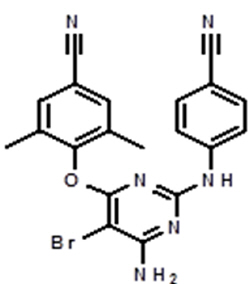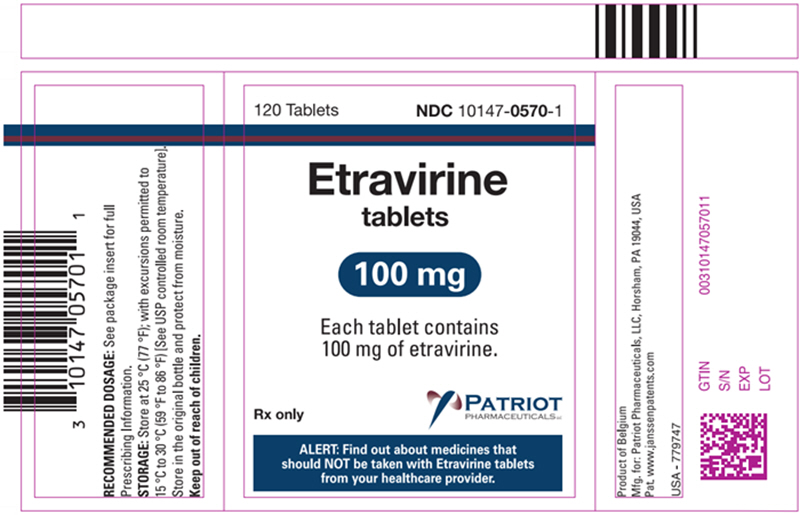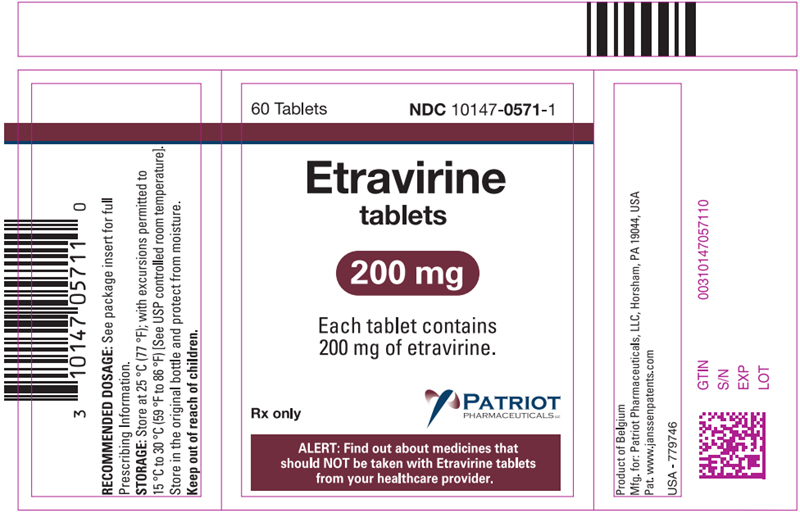 DRUG LABEL: Etravirine
NDC: 10147-0570 | Form: TABLET
Manufacturer: Patriot Pharmaceuticals
Category: prescription | Type: HUMAN PRESCRIPTION DRUG LABEL
Date: 20250402

ACTIVE INGREDIENTS: ETRAVIRINE 100 mg/1 1
INACTIVE INGREDIENTS: SILICON DIOXIDE; CROSCARMELLOSE SODIUM; HYPROMELLOSE, UNSPECIFIED; LACTOSE MONOHYDRATE; MAGNESIUM STEARATE; MICROCRYSTALLINE CELLULOSE

HIGHLIGHTS OF PRESCRIBING INFORMATION

These highlights do not include all the information needed to use Etravirine safely and effectively. See full prescribing information for Etravirine.
Etravirine tablets, for oral use
Initial U.S. Approval: 2008

1 INDICATIONS AND USAGE

Etravirine is a human immunodeficiency virus type 1 (HIV-1) non-nucleoside reverse transcriptase inhibitor (NNRTI) indicated for treatment of HIV-1 infection in treatment-experienced patients 2 years of age and older. (1)

2 DOSAGE AND ADMINISTRATION

- Adult patients: 200 mg (one 200 mg tablet or two 100 mg tablets) taken twice daily following a meal. (2.1, 2.2, 2.4)
- Pregnant patients: 200 mg (one 200 mg tablet or two 100 mg tablets) taken twice daily following a meal. (2.2)
- Pediatric patients (2 years to less than 18 years of age and weighing at least 10 kg): dosage of Etravirine is based on body weight and should not exceed the recommended adult dose. Etravirine tablets should be taken following a meal. (2.3)

3 DOSAGE FORMS AND STRENGTHS

- Tablets: 100 mg, and 200 mg (3)

4 CONTRAINDICATIONS

None.

5 WARNINGS AND PRECAUTIONS

- Severe, potentially life threatening and fatal skin reactions have been reported. This includes cases of Stevens-Johnson syndrome, hypersensitivity reaction, toxic epidermal necrolysis and erythema multiforme. Immediately discontinue treatment if severe hypersensitivity, severe rash or rash with systemic symptoms or liver transaminase elevations develops and monitor clinical status, including liver transaminases closely. (5.1)
- Monitor for immune reconstitution syndrome and fat redistribution. (5.3, 5.4)

6 ADVERSE REACTIONS

The most common adverse drug reactions of moderate to severe intensity (at least 2%) which occurred at a higher rate than placebo in adults are rash and peripheral neuropathy. (6.1)

The most common adverse drug reactions in at least 2% of pediatric patients are rash and diarrhea. (6.1)

To report SUSPECTED ADVERSE REACTIONS, contact Patriot Pharmaceuticals, LLC at 1-800-667-8570 or FDA at 1-800-FDA-1088 or www.fda.gov/medwatch.

7 DRUG INTERACTIONS

Co-administration of Etravirine with other drugs can alter the concentrations of other drugs and other drugs may alter the concentrations of etravirine. The potential drug-drug interactions must be considered prior to and during therapy. (7, 12.3)

8 USE IN SPECIFIC POPULATIONS

- Lactation: Breastfeeding is not recommended due to the potential for HIV-1 transmission. (8.2)

FULL PRESCRIBING INFORMATION

1 INDICATIONS AND USAGE

Etravirine, in combination with other antiretroviral agents, is indicated for the treatment of human immunodeficiency virus type 1 (HIV-1) infection in antiretroviral treatment-experienced adult patients and pediatric patients 2 years of age and older [see Microbiology (12.4)and Clinical Studies (14)] .

2 DOSAGE AND ADMINISTRATION

2.1 Recommended Dosage in Adult Patients

The recommended oral dosage of Etravirine for adult patients is 200 mg (one 200 mg tablet or two 100 mg tablets) taken twice daily following a meal. The type of food does not affect the exposure to Etravirine [see Clinical Pharmacology (12.3)] .

2.2 Recommended Dosage During Pregnancy

The recommended oral dosage of Etravirine for pregnant individuals is 200 mg (one 200 mg tablet or two 100 mg tablets) taken twice daily following a meal [see Use in Specific Populations (8.1)] .

2.3 Recommended Dosage in Pediatric Patients (2 Years to Less Than 18 Years of Age)

The recommended dosage of Etravirine for pediatric patients 2 years to less than 18 years of age and weighing at least 10 kg is based on body weight (see Table 1) not exceeding the recommended adult dosage. Etravirine should be taken orally, following a meal. The type of food does not affect the exposure to Etravirine [see Clinical Pharmacology (12.3)] .

Table 1: Recommended Dosage of Etravirine for Pediatric Patients 2 Years to Less Than 18 Years of Age
Body Weight kilograms (kg) | Dose
greater than or equal to 10 kg to less than 20 kg | 100 mg twice daily
greater than or equal to 20 kg to less than 25 kg | 125 mg twice daily
greater than or equal to 25 kg to less than 30 kg | 150 mg twice daily
greater than or equal to 30 kg | 200 mg twice daily

2.4 Method of Administration

Instruct patients to swallow the Etravirine tablet(s) whole with liquid such as water. Patients who are unable to swallow the Etravirine tablet(s) whole may disperse the tablet(s) in water. Instruct the patient to do the following:

- place the tablet(s) in 5 mL (1 teaspoon) of water, or at least enough liquid to cover the medication,
- stir well until the water looks milky,
- add approximately 15 mL (1 tablespoon) of liquid. Water may be used but other liquids, such as orange juice or milk, may improve taste. Patients should not place the tablets in orange juice or milk without first adding water. The use of warm (temperature greater than 104°F [greater than 40°C]) or carbonated beverages should be avoided.
- drink the mixture immediately,
- rinse the glass several times with orange juice, milk or water and completely swallow the rinse each time to make sure the patient takes the entire dose.

3 DOSAGE FORMS AND STRENGTHS

- 100 mg white to off-white oval tablets debossed with "TMC125" on one side and "100" on the other side.
- 200 mg white to off-white, biconvex, oblong tablets debossed with "T200" on one side.

4 CONTRAINDICATIONS

None.

5 WARNINGS AND PRECAUTIONS

5.1 Severe Skin and Hypersensitivity Reactions

Severe, potentially life-threatening and fatal skin reactions have been reported. In clinical trials, these include cases of Stevens-Johnson syndrome, toxic epidermal necrolysis and erythema multiforme. Hypersensitivity reactions including Drug Rash with Eosinophilia and Systemic Symptoms (DRESS) have also been reported and were characterized by rash, constitutional findings, and sometimes organ dysfunction, including hepatic failure. In Phase 3 clinical trials, Grade 3 and 4 rashes were reported in 1.3% of subjects receiving Etravirine compared to 0.2% of placebo subjects. A total of 2.2% of HIV-1-infected subjects receiving Etravirine discontinued from Phase 3 trials due to rash [see Adverse Reactions (6.1)] . Rash occurred most commonly during the first 6 weeks of therapy. The incidence of rash was higher in females [see Adverse Reactions (6.1)] . Stevens-Johnson syndrome was reported in 1.1% (2/177) of pediatric patients less than 18 years of age receiving Etravirine in combination with other HIV-1 antiretroviral agents in an observational study.

Discontinue Etravirine immediately if signs or symptoms of severe skin reactions or hypersensitivity reactions develop (including, but not limited to, severe rash or rash accompanied by fever, general malaise, fatigue, muscle or joint aches, blisters, oral lesions, conjunctivitis, facial edema, hepatitis, eosinophilia, angioedema). Clinical status including liver transaminases should be monitored and appropriate therapy initiated. Delay in stopping Etravirine treatment after the onset of severe rash may result in a life-threatening reaction.

5.2 Risk of Adverse Reactions or Loss of Virologic Response Due to Drug Interactions

The concomitant use of Etravirine and other drugs may result in potentially significant drug interactions, some of which may lead to [see Drug Interactions (7.3)] :

- Loss of therapeutic effect of concomitant drug or Etravirine and possible development of resistance.
- Possible clinically significant adverse reactions from greater exposures of Etravirine or other concomitant drugs.

See Table 4for steps to prevent or manage these possible and known significant drug interactions, including dosing recommendations. Consider the potential for drug interactions prior to and during Etravirine therapy and review concomitant medications during Etravirine therapy.

5.3 Immune Reconstitution Syndrome

Immune reconstitution syndrome has been reported in patients treated with combination antiretroviral therapy, including Etravirine. During the initial phase of combination antiretroviral treatment, patients whose immune system responds may develop an inflammatory response to indolent or residual opportunistic infections (such as Mycobacterium aviuminfection, cytomegalovirus, Pneumocystis jirovecipneumonia (PCP) or tuberculosis), which may necessitate further evaluation and treatment.

Autoimmune disorders (such as Graves' disease, polymyositis, Guillain-Barré syndrome, and autoimmune hepatitis) have also been reported to occur in the setting of immune reconstitution; however, the time to onset is more variable, and can occur many months after initiation of treatment.

5.4 Fat Redistribution

Redistribution/accumulation of body fat, including central obesity, dorsocervical fat enlargement (buffalo hump), peripheral wasting, facial wasting, breast enlargement, and "cushingoid appearance" have been observed in patients receiving antiretroviral therapy. The mechanism and long-term consequences of these events are currently unknown. A causal relationship has not been established.

6 ADVERSE REACTIONS

The following adverse reactions are described in greater detail in other sections:

- Severe skin and hypersensitivity reactions [see Warnings and Precautions (5.1)] .
- Immune reconstitution syndrome [see Warnings and Precautions (5.3)] .

6.1 Clinical Trials Experience

Because clinical trials are conducted under widely varying conditions, adverse reaction rates observed in the clinical trials of a drug cannot be directly compared to rates in the clinical trials of another drug and may not reflect the rates observed in practice.

Clinical Trials Experience in Adults

The safety assessment is based on all data from 1203 subjects in the Phase 3 placebo-controlled trials, TMC125-C206 and TMC125-C216, conducted in antiretroviral treatment-experienced HIV-1-infected adult subjects, 599 of whom received Etravirine (200 mg twice daily). In these pooled trials, the median exposure for subjects in the Etravirine arm and placebo arm was 52.3 and 51.0 weeks, respectively. Discontinuations due to adverse drug reactions (ADRs) were 5.2% in the Etravirine arm and 2.6% in the placebo arm.

The most frequently reported ADR at least Grade 2 in severity was rash (10.0%). Stevens-Johnson syndrome, drug hypersensitivity reaction and erythema multiforme were reported in less than 0.1% of subjects during clinical development with Etravirine [see Warnings and Precautions (5.1)] . A total of 2.2% of HIV-1-infected subjects in Phase 3 trials receiving Etravirine discontinued due to rash. In general, in clinical trials, rash was mild to moderate, occurred primarily in the second week of therapy, and was infrequent after Week 4. Rash generally resolved within 1 to 2 weeks on continued therapy. The incidence of rash was higher in women compared to men in the Etravirine arm in the Phase 3 trials (rash ≥ Grade 2 was reported in 9/60 [15.0%] women versus 51/539 [9.5%] men; discontinuations due to rash were reported in 3/60 [5.0%] women versus 10/539 [1.9%] men) [see Warnings and Precautions (5.1)] . Patients with a history of NNRTI-related rash did not appear to be at increased risk for the development of Etravirine-related rash compared to patients without a history of NNRTI-related rash.

Common Adverse Reactions

Clinical ADRs of moderate intensity or greater (greater than or equal to Grade 2) and reported in at least 2% of subjects treated with Etravirine and occurring at a higher rate compared to placebo (excess of 1%) are presented in Table 2. Laboratory abnormalities considered ADRs are included in Table 3.

Table 2: Adverse Drug Reactions (Grades 2 to 4) in at Least 2% of Adult Subjects (Pooled TMC125-C206 and TMC125-C216 Trials)
Preferred Term | Etravirine + BR N=599 % | Placebo + BR N=604 %
Rash | 10% | 3%
Peripheral neuropathy | 4% | 2%
N=total number of subjects per treatment group; BR=background regimen

Less Common Adverse Reactions

Treatment-emergent ADRs occurring in less than 2% of subjects (599 subjects) receiving Etravirine and of at least moderate intensity (greater than or equal to Grade 2) are listed below by body system:

Cardiac Disorders: myocardial infarction, angina pectoris, atrial fibrillation

Ear and Labyrinth Disorders: vertigo

Eye Disorders: blurred vision

Gastrointestinal Disorders: gastroesophageal reflux disease, flatulence, gastritis, abdominal distension, pancreatitis, constipation, dry mouth, hematemesis, retching, stomatitis

General Disorders and Administration Site Conditions: sluggishness

Hematologic Disorders: hemolytic anemia

Hepatobiliary Disorders: hepatic failure, hepatomegaly, cytolytic hepatitis, hepatic steatosis, hepatitis

Immune System Disorders: drug hypersensitivity, immune reconstitution syndrome

Metabolism and Nutrition Disorders: diabetes mellitus, anorexia, dyslipidemia

Nervous System Disorders: paresthesia, somnolence, convulsion, hypoesthesia, amnesia, syncope, disturbance in attention, hypersomnia, tremor

Psychiatric Disorders: anxiety, sleep disorders, abnormal dreams, confusional state, disorientation, nervousness, nightmares

Renal and Urinary Disorders:acute renal failure

Reproductive System and Breast Disorders: gynecomastia

Respiratory, Thoracic and Mediastinal Disorders: exertional dyspnea, bronchospasm

Skin and Subcutaneous Tissue Disorders: night sweats, lipohypertrophy, prurigo, hyperhidrosis, dry skin, swelling face

Additional ADRs of at least moderate intensity observed in other trials were acquired lipodystrophy, angioneurotic edema, erythema multiforme and hemorrhagic stroke, each reported in no more than 0.5% of subjects.

Laboratory Abnormalities in Treatment-Experienced Patients

Selected Grade 2 to Grade 4 laboratory abnormalities that represent a worsening from baseline observed in adult subjects treated with Etravirine are presented in Table 3.

Table 3: Selected Grade 2 to 4 Laboratory Abnormalities Observed in Treatment-Experienced Subjects (Pooled TMC125-C206 and TMC125-C216 Trials)
Laboratory Parameter | DAIDS Toxicity Range | Etravirine + BR N=599 % | Placebo + BR N=604 %
GENERAL BIOCHEMISTRY
Pancreatic amylase
Grade 2 | > 1.5–2 × ULN | 7% | 8%
Grade 3 | > 2–5 × ULN | 7% | 8%
Grade 4 | > 5 × ULN | 2% | 1%
Lipase
Grade 2 | > 1.5–3 × ULN | 4% | 6%
Grade 3 | > 3–5 × ULN | 2% | 2%
Grade 4 | > 5 × ULN | 1% | < 1%
Creatinine
Grade 2 | > 1.4–1.8 × ULN | 6% | 5%
Grade 3 | > 1.9–3.4 × ULN | 2% | 1%
Grade 4 | > 3.4 × ULN | 0% | < 1%
HEMATOLOGY
Decreased hemoglobin
Grade 2 | 90–99 g/L | 2% | 4%
Grade 3 | 70–89 g/L | < 1% | < 1%
Grade 4 | < 70 g/L | < 1% | < 1%
White blood cell count
Grade 2 | 1,500–1,999/mm^3 | 2% | 3%
Grade 3 | 1,000–1,499/mm^3 | 1% | 4%
Grade 4 | < 1,000/mm^3 | 1% | < 1%
Neutrophils
Grade 2 | 750–999/mm^3 | 5% | 6%
Grade 3 | 500–749/mm^3 | 4% | 4%
Grade 4 | < 500/mm^3 | 2% | 3%
Platelet count
Grade 2 | 50,000–99,999/mm^3 | 3% | 5%
Grade 3 | 25,000–49,999/mm^3 | 1% | 1%
Grade 4 | < 25,000/mm^3 | < 1% | < 1%
LIPIDS AND GLUCOSE
Total cholesterol
Grade 2 | > 6.20–7.77 mmol/L 240–300 mg/dL | 20% | 17%
Grade 3 | > 7.77 mmol/L > 300 mg/dL | 8% | 5%
Low density lipoprotein
Grade 2 | 4.13–4.9 mmol/L 160–190 mg/dL | 13% | 12%
Grade 3 | > 4.9 mmol/L > 190 mg/dL | 7% | 7%
Triglycerides
Grade 2 | 5.65–8.48 mmol/L 500–750 mg/dL | 9% | 7%
Grade 3 | 8.49–13.56 mmol/L 751–1200 mg/dL | 6% | 4%
Grade 4 | > 13.56 mmol/L > 1200 mg/dL | 4% | 2%
Elevated glucose levels
Grade 2 | 6.95–13.88 mmol/L 161–250 mg/dL | 15% | 13%
Grade 3 | 13.89–27.75 mmol/L 251–500 mg/dL | 4% | 2%
Grade 4 | > 27.75 mmol/L > 500 mg/dL | 0% | < 1%
HEPATIC PARAMETERS
Alanine amino transferase
Grade 2 | 2.6–5 × ULN | 6% | 5%
Grade 3 | 5.1–10 × ULN | 3% | 2%
Grade 4 | > 10 × ULN | 1% | < 1%
Aspartate amino transferase
Grade 2 | 2.6–5 × ULN | 6% | 8%
Grade 3 | 5.1–10 × ULN | 3% | 2%
Grade 4 | > 10 × ULN | < 1% | < 1%
ULN=Upper Limit of Normal; BR=background regimen

Patients Co-Infected With Hepatitis B and/or Hepatitis C Virus

In Phase 3 trials TMC125-C206 and TMC125-C216, 139 subjects (12.3%) with chronic hepatitis B and/or hepatitis C virus co-infection out of 1129 subjects were permitted to enroll. AST and ALT abnormalities occurred more frequently in hepatitis B and/or hepatitis C virus co-infected subjects for both treatment groups. Grade 2 or higher laboratory abnormalities that represent a worsening from baseline of AST, ALT or total bilirubin occurred in 27.8%, 25.0% and 7.1% respectively, of Etravirine-treated co-infected subjects as compared to 6.7%, 7.5% and 1.8% of non-co-infected Etravirine-treated subjects. In general, adverse events reported by Etravirine-treated subjects with hepatitis B and/or hepatitis C virus co-infection were similar to Etravirine-treated subjects without hepatitis B and/or hepatitis C virus co-infection.

Clinical Trials Experience in Pediatric Subjects (2 Years to Less Than 18 years of age)

The safety assessment in pediatric subjects is based on two single-arm trials. TMC125-C213 is a Phase 2 trial in which 101 antiretroviral treatment-experienced HIV-1 infected pediatric subjects 6 years to less than 18 years of age received Etravirine in combination with other antiretroviral agents (Week 24 analysis). TMC125-C234/IMPAACT P1090 is a Phase 1/2 trial in which 20 antiretroviral treatment-experienced HIV-1 infected pediatric subjects 2 years to less than 6 years of age received Etravirine in combination with other antiretroviral agents (Week 24 analysis) [see Clinical Studies (14.2)] .

In TMC125-C213, the frequency, type and severity of adverse drug reactions in pediatric subjects 6 years to less than 18 years of age were comparable to those observed in adult subjects, except for rash which was observed more frequently in pediatric subjects. The most common adverse drug reactions in at least 2% of pediatric subjects were rash and diarrhea. Rash was reported more frequently in female subjects than in male subjects (rash ≥ Grade 2 was reported in 13/64 [20.3%] females versus 2/37 [5.4%] males; discontinuations due to rash were reported in 4/64 [6.3%] females versus 0/37 [0%] males). Rash (greater than or equal to Grade 2) occurred in 15% of pediatric subjects from 6 years to less than 18 years of age. In the majority of cases, rash was mild to moderate, of macular/papular type, and occurred in the second week of therapy. Rash was self-limiting and generally resolved within 1 week on continued therapy. The safety profile for subjects who completed 48 weeks of treatment was similar to the safety profile for subjects who completed 24 weeks of treatment.

In TMC125-C234/IMPAACT P1090, the frequency, type and severity of adverse drug reactions in pediatric subjects 2 years to less than 6 years of age through Week 24 were comparable to those observed in adults. The most common adverse drug reactions (any grade) of pediatric subjects were rash (50% [10/20]) and diarrhea (25% [5/20]). In this age group, no subjects had Grade 3 or Grade 4 rash and no subjects discontinued prematurely due to rash. One subject discontinued etravirine due to asymptomatic lipase elevation.

6.2 Postmarketing Experience

The following events have been identified during postmarketing use of Etravirine. Because these events are reported voluntarily from a population of unknown size, it is not always possible to reliably estimate their frequency or establish a causal relationship to drug exposure.

Immune System Disorders: Severe hypersensitivity reactions including DRESS and cases of hepatic failure have been reported [see Warnings and Precautions (5.1)] .

Musculoskeletal and Connective Tissue Disorders: rhabdomyolysis

Skin and Subcutaneous Tissue Disorders: Fatal cases of toxic epidermal necrolysis and Stevens-Johnson syndrome have been reported [see Warnings and Precautions (5.1)] .

7 DRUG INTERACTIONS

7.1 Potential for Other Drugs to Affect Etravirine

Etravirine is a substrate of CYP3A, CYP2C9, and CYP2C19. Therefore, co-administration of Etravirine with drugs that induce or inhibit CYP3A, CYP2C9, and CYP2C19 may alter the therapeutic effect or adverse reaction profile of Etravirine (see Table 4) [see Clinical Pharmacology (12.3)].

7.2 Potential for Etravirine to Affect Other Drugs

Etravirine is an inducer of CYP3A and inhibitor of CYP2C9, CYP2C19 and P-glycoprotein (P-gp). Therefore, co-administration of drugs that are substrates of CYP3A, CYP2C9 and CYP2C19 or are transported by P-gp with Etravirine may alter the therapeutic effect or adverse reaction profile of the co-administered drug(s) (see Table 4) [see Clinical Pharmacology (12.3)].

7.3 Significant Drug Interactions

Table 4 shows significant drug interactions based on which, alterations in dose or regimen of Etravirine and/or co-administered drug may be recommended. Drugs that are not recommended for co-administration with Etravirine are also included in Table 4 [see Clinical Pharmacology (12.3)] .

Table 4: Significant Drug Interactions
Concomitant Drug Class: Drug Name | Effect on Concentration of Etravirine or Concomitant Drug | Clinical Comment
HIV-antiviral agents: integrase strand inhibitors
dolutegravir [The interaction between Etravirine and the drug was evaluated in a clinical study. All other drug interactions shown are predicted.] | ↓ dolutegravir ↔ etravirine | Etravirine significantly reduced plasma concentrations of dolutegravir. Using cross -study comparisons to historical pharmacokinetic data for etravirine, dolutegravir did not appear to affect the pharmacokinetics of etravirine.
dolutegravir/darunavir /ritonavir | ↓ dolutegravir ↔ etravirine | The effect of etravirine on dolutegravir plasma concentrations was mitigated by co-administration of darunavir/ritonavir or lopinavir/ritonavir, and is expected to be mitigated by atazanavir/ritonavir. Dolutegravir should only be used with Etravirine when co-administered with atazanavir/ritonavir, darunavir/ritonavir, or lopinavir/ritonavir.
dolutegravir/lopinavir /ritonavir | ↔ dolutegravir ↔ etravirine | The effect of etravirine on dolutegravir plasma concentrations was mitigated by co-administration of darunavir/ritonavir or lopinavir/ritonavir, and is expected to be mitigated by atazanavir/ritonavir. Dolutegravir should only be used with Etravirine when co-administered with atazanavir/ritonavir, darunavir/ritonavir, or lopinavir/ritonavir.
HIV-antiviral agents: non-nucleoside reverse transcriptase inhibitors (NNRTIs)
efavirenz nevirapine | ↓ etravirine | Combining two NNRTIs has not been shown to be beneficial. Concomitant use of Etravirine with efavirenz or nevirapine may cause a significant decrease in the plasma concentrations of etravirine and loss of therapeutic effect of Etravirine. Co-administration of Etravirine and other NNRTIs is not recommended.
delavirdine | ↑ etravirine | Combining two NNRTIs has not been shown to be beneficial. Etravirine and delavirdine should not be co-administered.
rilpivirine | ↓ rilpivirine ↔ etravirine | Combining two NNRTIs has not been shown to be beneficial. Co-administration of Etravirine and rilpivirine is not recommended.
HIV-antiviral agents: protease inhibitors (PIs)
atazanavir (without ritonavir) | ↓ atazanavir | Co-administration of Etravirine and atazanavir without low-dose ritonavir is not recommended.
atazanavir/ritonavir | ↓ atazanavir ↔ etravirine | Concomitant use of Etravirine with atazanavir/ritonavir decreased atazanavir Cminbut it is not considered clinically relevant. The mean systemic exposure (AUC) of etravirine after co-administration of Etravirine with atazanavir/ritonavir in HIV-infected subjects was similar to the mean systemic exposure of etravirine observed in the Phase 3 trials after co-administration of Etravirine and darunavir/ritonavir (as part of the background regimen). Etravirine and atazanavir/ritonavir can be co-administered without dose adjustments.
atazanavir/cobicistat | ↓ atazanavir ↓ cobicistat | Co-administration of Etravirine with atazanavir/cobicistat is not recommended because it may result in loss of therapeutic effect and development of resistance to atazanavir.
darunavir/ritonavir | ↓ etravirine | The mean systemic exposure (AUC) of etravirine was reduced when Etravirine was co-administered with darunavir/ritonavir. Because all subjects in the Phase 3 trials received darunavir/ritonavir as part of the background regimen and etravirine exposures from these trials were determined to be safe and effective, Etravirine and darunavir/ritonavir can be co-administered without dose adjustments.
darunavir/cobicistat | ↓ cobicistat darunavir: effect unknown | Co-administration of Etravirine with darunavir/cobicistat is not recommended because it may result in loss of therapeutic effect and development of resistance to darunavir.
fosamprenavir (without ritonavir) | ↑ amprenavir | Concomitant use of Etravirine with fosamprenavir without low-dose ritonavir may cause a significant alteration in the plasma concentration of amprenavir. Co-administration of Etravirine and fosamprenavir without low-dose ritonavir is not recommended.
fosamprenavir/ritonavir | ↑ amprenavir | Due to a significant increase in the systemic exposure of amprenavir, the appropriate doses of the combination of Etravirine and fosamprenavir/ritonavir have not been established. Co-administration of Etravirine and fosamprenavir/ritonavir is not recommended.
indinavir (without ritonavir) | ↓ indinavir | Concomitant use of Etravirine with indinavir without low-dose ritonavir may cause a significant alteration in the plasma concentration of indinavir. Co-administration of Etravirine and indinavir without low-dose ritonavir is not recommended.
lopinavir/ritonavir | ↓ etravirine | The mean systemic exposure (AUC) of etravirine was reduced after co-administration of Etravirine with lopinavir/ritonavir (tablet). Because the reduction in the mean systemic exposures of etravirine in the presence of lopinavir/ritonavir is similar to the reduction in mean systemic exposures of etravirine in the presence of darunavir/ritonavir, Etravirine and lopinavir/ritonavir can be co-administered without dose adjustments.
nelfinavir (without ritonavir) | ↑ nelfinavir | Concomitant use of Etravirine with nelfinavir without low-dose ritonavir may cause a significant alteration in the plasma concentration of nelfinavir. Co-administration of Etravirine and nelfinavir without low-dose ritonavir is not recommended.
ritonavir | ↓ etravirine | Concomitant use of Etravirine with ritonavir 600 mg twice daily may cause a significant decrease in the plasma concentration of etravirine and loss of therapeutic effect of Etravirine. Co-administration of Etravirine and ritonavir 600 mg twice daily is not recommended.
saquinavir/ritonavir | ↓ etravirine | The mean systemic exposure (AUC) of etravirine was reduced when Etravirine was co-administered with saquinavir/ritonavir. Because the reduction in the mean systemic exposures of etravirine in the presence of saquinavir/ritonavir is similar to the reduction in mean systemic exposures of etravirine in the presence of darunavir/ritonavir, Etravirine and saquinavir/ritonavir can be co-administered without dose adjustments.
tipranavir/ritonavir | ↓ etravirine | Concomitant use of Etravirine with tipranavir/ritonavir may cause a significant decrease in the plasma concentrations of etravirine and loss of therapeutic effect of Etravirine. Co-administration of Etravirine and tipranavir/ritonavir is not recommended.
CCR5 antagonists
maraviroc | ↔ etravirine ↓ maraviroc | When Etravirine is co-administered with maraviroc in the absence of a potent CYP3A inhibitor (e.g., ritonavir boosted protease inhibitor), the recommended dose of maraviroc is 600 mg twice daily. No dose adjustment of Etravirine is needed.
maraviroc/darunavir/ ritonavir [The reference for etravirine exposure is the pharmacokinetic parameters of etravirine in the presence of darunavir/ritonavir.] | ↔ etravirine ↑ maraviroc | When Etravirine is co-administered with maraviroc in the presence of a potent CYP3A inhibitor (e.g., ritonavir boosted protease inhibitor), the recommended dose of maraviroc is 150 mg twice daily. No dose adjustment of Etravirine is needed.
Other agents
Antiarrhythmics: digoxin | ↔ etravirine ↑ digoxin | For patients who are initiating a combination of Etravirine and digoxin, the lowest dose of digoxin should initially be prescribed. For patients on a stable digoxin regimen and initiating Etravirine, no dose adjustment of either Etravirine or digoxin is needed. The serum digoxin concentrations should be monitored and used for titration of the digoxin dose to obtain the desired clinical effect.
amiodarone bepridil disopyramide flecainide lidocaine (systemic) mexiletine propafenone quinidine | ↓ antiarrhythmics | Concentrations of these antiarrhythmics may be decreased when co-administered with Etravirine. Etravirine and antiarrhythmics should be co-administered with caution. Drug concentration monitoring is recommended, if available.
Anticoagulant: warfarin | ↑ anticoagulants | Warfarin concentrations may be increased when co-administered with Etravirine. The international normalized ratio (INR) should be monitored when warfarin is combined with Etravirine.
Anticonvulsants: carbamazepine phenobarbital phenytoin | ↓ etravirine | Carbamazepine, phenobarbital and phenytoin are inducers of CYP450 enzymes. Etravirine should not be used in combination with carbamazepine, phenobarbital, or phenytoin as co-administration may cause significant decreases in etravirine plasma concentrations and loss of therapeutic effect of Etravirine.
Antifungals: fluconazole | ↑ etravirine ↔ fluconazole | Co-administration of etravirine and fluconazole significantly increased etravirine exposures. The amount of safety data at these increased etravirine exposures is limited, therefore, etravirine and fluconazole should be co-administered with caution. No dose adjustment of Etravirine or fluconazole is needed.
voriconazole | ↑ voriconazole | Co-administration of etravirine and voriconazole significantly increased etravirine exposures. The amount of safety data at these increased etravirine exposures is limited, therefore, etravirine and voriconazole should be co-administered with caution. No dose adjustment of Etravirine or voriconazole is needed.
Antifungals: itraconazole ketoconazole posaconazole | ↑ etravirine ↓ itraconazole ↓ ketoconazole ↔ posaconazole | Posaconazole, a potent inhibitor of CYP3A4, may increase plasma concentrations of etravirine. Itraconazole and ketoconazole are potent inhibitors as well as substrates of CYP3A4. Concomitant systemic use of itraconazole or ketoconazole and Etravirine may increase plasma concentrations of etravirine. Simultaneously, plasma concentrations of itraconazole or ketoconazole may be decreased by Etravirine. Dose adjustments for itraconazole, ketoconazole or posaconazole may be necessary depending on the other co-administered drugs.
Antiinfective: clarithromycin | ↑ etravirine ↓ clarithromycin ↑ 14-OH-clarithromycin | Clarithromycin exposure was decreased by Etravirine; however, concentrations of the active metabolite, 14-hydroxy-clarithromycin, were increased. Because 14-hydroxy-clarithromycin has reduced activity against Mycobacterium aviumcomplex (MAC), overall activity against this pathogen may be altered. Alternatives to clarithromycin, such as azithromycin, should be considered for the treatment of MAC.
Antimalarial: artemether/lumefantrine | ↔ etravirine ↓ artemether ↓ dihydroartemisinin ↓ lumefantrine | Caution is warranted when co-administering Etravirine and artemether/lumefantrine as it is unknown whether the decrease in exposure of artemether or its active metabolite, dihydroartemisinin, could result in decreased antimalarial efficacy. No dose adjustment is needed for Etravirine.
Antimycobacterials: rifampin rifapentine | ↓ etravirine | Rifampin and rifapentine are potent inducers of CYP450 enzymes. Etravirine should not be used with rifampin or rifapentine as co-administration may cause significant decreases in etravirine plasma concentrations and loss of therapeutic effect of Etravirine.
Antimycobacterial: rifabutin | ↓ etravirine ↓ rifabutin ↓ 25- O-desacetylrifabutin | If Etravirine is NOT co-administered with a protease inhibitor/ritonavir, then rifabutin at a dose of 300 mg once daily is recommended.
 |  | If Etravirine is co-administered with darunavir/ritonavir, lopinavir/ritonavir or saquinavir/ritonavir, then rifabutin should not be co-administered due to the potential for significant reductions in etravirine exposure.
Benzodiazepine: diazepam | ↑ diazepam | Concomitant use of Etravirine with diazepam may increase plasma concentrations of diazepam. A decrease in diazepam dose may be needed.
Corticosteroid: dexamethasone (systemic) | ↓ etravirine | Systemic dexamethasone induces CYP3A and can decrease etravirine plasma concentrations. This may result in loss of therapeutic effect of Etravirine. Systemic dexamethasone should be used with caution or alternatives should be considered, particularly for long-term use.
Herbal products: St. John's wort (Hypericum perforatum) | ↓ etravirine | Concomitant use of Etravirine with products containing St. John's wort may cause significant decreases in etravirine plasma concentrations and loss of therapeutic effect of Etravirine. Etravirine and products containing St. John's wort should not be co-administered.
Hepatitis C virus (HCV) direct-acting antivirals: daclatasvir | ↓ daclatasvir | Co-administration of Etravirine with daclatasvir may decrease daclatasvir concentrations. Increase the daclatasvir dose to 90 mg once daily.
elbasvir/grazoprevir | ↓ elbasvir ↓ grazoprevir | Co-administration of Etravirine with elbasvir/grazoprevir may decrease elbasvir and grazoprevir concentrations, leading to reduced therapeutic effect of elbasvir/grazoprevir. Co-administration is not recommended.
HMG-CoA reductase inhibitors: atorvastatin | ↔ etravirine ↓ atorvastatin ↑ 2-OH-atorvastatin | The combination of Etravirine and atorvastatin can be given without dose adjustments, however, the dose of atorvastatin may need to be altered based on clinical response.
pravastatin rosuvastatin | ↔ etravirine ↔ pravastatin ↔ rosuvastatin | No interaction between pravastatin, rosuvastatin and Etravirine is expected.
lovastatin simvastatin | ↓ lovastatin ↓ simvastatin | Lovastatin and simvastatin are CYP3A substrates and co-administration with Etravirine may result in lower plasma concentrations of the HMG-CoA reductase inhibitor.
fluvastatin pitavastatin | ↑ fluvastatin ↑ pitavastatin | Fluvastatin and pitavastatin are metabolized by CYP2C9 and co-administration with Etravirine may result in higher plasma concentrations of the HMG-CoA reductase inhibitor. Dose adjustments for these HMG-CoA reductase inhibitors may be necessary.
Immunosuppressants: cyclosporine sirolimus tacrolimus | ↓ immunosuppressant | Etravirine and systemic immunosuppressants should be co-administered with caution because plasma concentrations of cyclosporine, sirolimus, or tacrolimus may be affected.
Narcotic analgesics/treatment of opioid dependence: buprenorphine buprenorphine/naloxone methadone | ↔ etravirine ↓ buprenorphine ↔ norbuprenorphine ↔ methadone | Etravirine and buprenorphine (or buprenorphine/naloxone) can be co-administered without dose adjustments, however, clinical monitoring for withdrawal symptoms is recommended as buprenorphine (or buprenorphine/naloxone) maintenance therapy may need to be adjusted in some patients.
 |  | Etravirine and methadone can be co-administered without dose adjustments, however, clinical monitoring for withdrawal symptoms is recommended as methadone maintenance therapy may need to be adjusted in some patients.
Phosphodiesterase type 5 (PDE-5) inhibitors: sildenafil tadalafil vardenafil | ↓ sildenafil ↓ N-desmethyl-sildenafil | Etravirine and sildenafil can be co-administered without dose adjustments, however, the dose of sildenafil may need to be altered based on clinical effect.
Platelet aggregation inhibitors: clopidogrel | ↓ clopidogrel (active) metabolite | Activation of clopidogrel to its active metabolite may be decreased when clopidogrel is co-administered with Etravirine. Alternatives to clopidogrel should be considered.
↑ = increase; ↓ = decrease; ↔ = no change

7.4 Drugs Without Clinically Significant Interactions with Etravirine

In addition to the drugs included in Table 4, the interaction between Etravirine and the following drugs were evaluated in clinical studies and no dose adjustment is needed for either drug [see Clinical Pharmacology (12.3)] : didanosine, enfuvirtide (ENF), ethinylestradiol/norethindrone, omeprazole, paroxetine, raltegravir, ranitidine, and tenofovir disoproxil fumarate.

8 USE IN SPECIFIC POPULATIONS

8.1 Pregnancy

Pregnancy Exposure Registry

There is a pregnancy exposure registry that monitors pregnancy outcomes in individuals exposed to Etravirine during pregnancy. Healthcare providers are encouraged to register patients by calling the Antiretroviral Pregnancy Registry (APR) at 1-800-258-4263.

Risk Summary

Prospective pregnancy data from clinical trials and the APR are not sufficient to adequately assess the risk of major birth defects, miscarriage or adverse maternal or fetal outcomes. Etravirine use during pregnancy has been evaluated in a limited number of individuals as reported by the APR, and available data show 1 birth defect in 66 first trimester exposures to etravirine-containing regimens (see Data) .

The estimated background rate for major birth defects is 2.7% in the U.S. reference population of the Metropolitan Atlanta Congenital Defects Program (MACDP). The rate of miscarriage is not reported in the APR. The estimated background rate of miscarriage in clinically recognized pregnancies in the U.S. general population is 15–20%. The background risk of major birth defects and miscarriage for the indicated population is unknown.

In animal reproduction studies, no adverse developmental effects were observed with orally administered etravirine at exposures equivalent to those at the maximum recommended human dose (MRHD) of 400 mg daily (see Data) .

Data

Human Data

Based on prospective reports to the APR of 116 live births following exposure to etravirine-containing regimens during pregnancy (including 66 exposed in the first trimester and 38 exposed in the second/third trimester), the number of birth defects in live births for etravirine was 1 out of 66 with first trimester exposure and 0 out of 38 with second/third trimester exposure. Prospective reports from the APR of overall major birth defects in pregnancies exposed to Etravirine is compared with a U.S. background major birth defect rate. Methodological limitations of the APR include the use of MACDP as the external comparator group. Limitations of using an external comparator include differences in methodology and populations, as well as confounding due to the underlying disease; these limitations preclude an accurate comparison of outcomes.

Etravirine (200 mg twice daily) in combination with other antiretroviral agents was evaluated in a clinical trial enrolling 15 pregnant subjects during the second and third trimesters of pregnancy and postpartum. Thirteen subjects completed the trial through postpartum period (6–12 weeks after delivery). The pharmacokinetic data demonstrated that exposure to total etravirine was generally higher during pregnancy compared with postpartum [see Clinical Pharmacology (12.3)] .

Among subjects who were virologically suppressed (HIV-1 RNA less than 50 copies/mL) at baseline (9/13), virologic suppression was maintained through the third trimester and postpartum period. Among subjects with HIV-1 RNA greater than 50 copies/mL and less than 400 copies/mL at baseline (3/13), viral loads remained less than 400 copies/mL. In one subject with HIV-1 RNA greater than 1,000 copies/mL at baseline (1/13), HIV-1 RNA remained greater than 1,000 copies/mL during the study period. Thirteen infants were born to 13 HIV-infected pregnant individuals in this study. HIV-1 test results were not available for 2 infants. Among the eleven infants with HIV-1 test results available, who were born to 11 HIV-infected pregnant individuals who completed the study, all had test results that were negative for HIV-1 at the time of delivery. No unexpected safety findings were observed compared with the known safety profile of Etravirine in non-pregnant adults.

Animal Data

Reproductive and developmental toxicity studies were performed in rats (at 250, 500 and 1,000 mg/kg/day) and rabbits (at 125, 250 and 375 mg/kg/day) administered etravirine on gestation days 6 through 16, and 6 through 19, respectively. In both species, no treatment-related embryo-fetal effects were observed. In addition, no treatment-related effects were observed in a pre- and postnatal development study performed in rats administered oral doses up to 500 mg/kg/day on gestation days 7 through lactation day 7. The systemic drug exposures achieved at the high dose in these animal studies were equivalent to those at the MRHD.

8.2 Lactation

Risk Summary

The Centers for Disease Control and Prevention recommend that HIV-1-infected mothers not breastfeed their infants to avoid risking postnatal transmission of HIV.

Based on limited data, etravirine has been shown to be present in human breast milk. There are no data on the effects of etravirine on the breastfed infant, or the effects of etravirine on milk production.

Because of the potential for (1) HIV-1 transmission (in HIV-negative infants), (2) developing viral resistance (in HIV-positive infants) and (3) adverse reactions in breastfed infants similar to those seen in adults, instruct mothers not to breastfeed if they are receiving Etravirine.

8.4 Pediatric Use

The safety and effectiveness of Etravirine have been established for the treatment of HIV-infected pediatric patients from 2 years of age to less than 18 years [see Indications and Usage (1)and Dosage and Administration (2.3)] . Use of Etravirine in pediatric patients 2 years to less than 18 years of age is supported by evidence from adequate and well-controlled studies of Etravirine in adults with additional data from two Phase 2 trials in treatment-experienced pediatric subjects, TMC125-C213, 6 years to less than 18 years of age (N=101) and TMC125-C234/IMPAACT P1090, 2 years to less than 6 years of age (N=20). Both studies were open-label, single arm trials of etravirine plus an optimized background regimen. In clinical trials, the safety, pharmacokinetics, and efficacy were comparable to that observed in adults except for rash (greater than or equal to Grade 2) which was observed more frequently in pediatric subjects [see Adverse Reactions (6.1), Clinical Pharmacology (12.3), and Clinical Studies (14.2)] . Postmarketing reports of Stevens-Johnson syndrome in pediatric patients receiving Etravirine have been reported [see Warnings and Precautions (5.1), and Adverse Reactions (6.2)] .

Treatment with Etravirine is not recommended in pediatric patients less than 2 years of age [see Clinical Pharmacology (12.3)] . Five HIV-infected subjects from 1 year to < 2 years of age were enrolled in TMC125-C234/IMPAACT P1090. Etravirine exposure was lower than reported in HIV-infected adults (AUC12hgeometric mean ratio [90% CI] was 0.59 [0.34, 1.01] for pediatric subjects from 1 year to < 2 years of age compared to adults). Virologic failure at Week 24 (confirmed HIV-RNA greater than or equal to 400 copies/mL) occurred in 3 of 4 evaluable subjects who discontinued before or had reached Week 24. Genotypic and phenotypic resistance to etravirine developed in 1 of the 3 subjects who experienced virologic failure.

8.5 Geriatric Use

Clinical studies of Etravirine did not include sufficient numbers of subjects aged 65 years of age and over to determine whether they respond differently from younger subjects. Other reported clinical experience has not identified differences in responses between the elderly and younger subjects. In general, dose selection for an elderly patient should be cautious, reflecting the greater frequency of decreased hepatic, renal, or cardiac function, and of concomitant disease or other drug therapy [see Clinical Pharmacology (12.3)] .

8.6 Hepatic Impairment

No dose adjustment of Etravirine is required in patients with mild (Child-Pugh Class A) or moderate (Child-Pugh Class B) hepatic impairment. The pharmacokinetics of Etravirine have not been evaluated in patients with severe hepatic impairment (Child-Pugh Class C) [see Clinical Pharmacology (12.3)] .

8.7 Renal Impairment

Since the renal clearance of etravirine is negligible (less than 1.2%), a decrease in total body clearance is not expected in patients with renal impairment. No dose adjustments are required in patients with renal impairment. As etravirine is highly bound to plasma proteins, it is unlikely that it will be significantly removed by hemodialysis or peritoneal dialysis [see Clinical Pharmacology (12.3)] .

10 OVERDOSAGE

There is no specific antidote for overdose with Etravirine. Human experience of overdose with Etravirine is limited. The highest dose studied in healthy volunteers was 400 mg once daily. Treatment of overdose with Etravirine consists of general supportive measures including monitoring of vital signs and observation of the clinical status of the patient. Because etravirine is highly protein bound, dialysis is unlikely to result in significant removal of the active substance.

11 DESCRIPTION

Etravirine is a non-nucleoside reverse transcriptase inhibitor (NNRTI) of human immunodeficiency virus type 1 (HIV-1).

The chemical name for etravirine is 4-[[6-amino-5-bromo-2-[(4-cyanophenyl)amino]-4- pyrimidinyl]oxy]-3,5-dimethylbenzonitrile. Its molecular formula is C20H15BrN6O and its molecular weight is 435.28. Etravirine has the following structural formula:

Etravirine is a white to slightly yellowish-brown powder. Etravirine is practically insoluble in water over a wide pH range. It is very slightly soluble in propylene glycol and slightly soluble in ethanol. Etravirine is soluble in polyethylene glycol (PEG)400 and freely soluble in some organic solvents (e.g., N,N-dimethylformamide and tetrahydrofuran).

Etravirine 100 mg tablets are available as white to off-white, oval tablets for oral administration. Each 100 mg tablet contains 100 mg of etravirine and the inactive ingredients colloidal silicon dioxide, croscarmellose sodium, hypromellose, lactose monohydrate, magnesium stearate and microcrystalline cellulose.

Etravirine 200 mg tablets are available as white to off-white, biconvex, oblong tablets for oral administration. Each 200 mg tablet contains 200 mg of etravirine and the inactive ingredients colloidal silicon dioxide, croscarmellose sodium, hypromellose, magnesium stearate, microcrystalline cellulose and silicified microcrystalline cellulose.

12 CLINICAL PHARMACOLOGY

12.1 Mechanism of Action

Etravirine is an antiretroviral drug [see Microbiology (12.4)] .

12.2 Pharmacodynamics

Cardiac Electrophysiology

In a thorough QT/QTc study in 41 healthy subjects, Etravirine 200 mg twice daily or 400 mg once daily did not affect the QT/QTc interval.

12.3 Pharmacokinetics

The pharmacokinetic properties of Etravirine were determined in healthy adult subjects and in treatment-experienced HIV-1-infected adult and pediatric subjects. The systemic exposures (AUC) to etravirine were lower in HIV-1-infected subjects (Table 5) than in healthy subjects.

Table 5: Population Pharmacokinetic Estimates of Etravirine 200 mg Twice Daily in HIV-1-Infected Adult Subjects (Integrated Data from Phase 3 Trials at Week 48) [All HIV-1-infected subjects enrolled in Phase 3 clinical trials received darunavir/ritonavir 600/100 mg twice daily as part of their background regimen. Therefore, the pharmacokinetic parameter estimates shown in Table 5 account for reductions in the pharmacokinetic parameters of etravirine due to co-administration of Etravirine with darunavir/ritonavir.]
Parameter | Etravirine N=575
AUC12h(ng∙h/mL)
Geometric mean ± standard deviation | 4522 ± 4710
Median (range) | 4380 (458–59084)
C0h(ng/mL)
Geometric mean ± standard deviation | 297 ± 391
Median (range) | 298 (2–4852)

Note: The median protein binding adjusted EC50for MT4 cells infected with HIV-1/IIIB in vitroequals 4 ng/mL.

Absorption and Bioavailability

Following oral administration, etravirine was absorbed with a Tmaxof about 2.5 to 4 hours. The absolute oral bioavailability of Etravirine is unknown.

In healthy subjects, the absorption of etravirine is not affected by co-administration of oral ranitidine or omeprazole, drugs that increase gastric pH.

Effects of Food on Oral Absorption

The systemic exposure (AUC) to etravirine was decreased by about 50% when Etravirine was administered under fasting conditions, as compared to when Etravirine was administered following a meal. Within the range of meals studied, the systemic exposures to etravirine were similar. The total caloric content of the various meals evaluated ranged from 345 kilocalories (17 grams fat) to 1160 kilocalories (70 grams fat).

Distribution

Etravirine is about 99.9% bound to plasma proteins, primarily to albumin (99.6%) and alpha 1-acid glycoprotein (97.66% to 99.02%) in vitro. The distribution of etravirine into compartments other than plasma (e.g., cerebrospinal fluid, genital tract secretions) has not been evaluated in humans.

Metabolism

In vitroexperiments with human liver microsomes (HLMs) indicate that etravirine primarily undergoes metabolism by CYP3A, CYP2C9, and CYP2C19 enzymes. The major metabolites, formed by methyl hydroxylation of the dimethylbenzonitrile moiety, were at least 90% less active than etravirine against wild-type HIV in cell culture.

Elimination

After single dose oral administration of 800 mg^14C-etravirine, 93.7% and 1.2% of the administered dose of^14C-etravirine was recovered in the feces and urine, respectively. Unchanged etravirine accounted for 81.2% to 86.4% of the administered dose in feces. Unchanged etravirine was not detected in urine. The mean (± standard deviation) terminal elimination half-life of etravirine was about 41 (± 20) hours.

Specific Populations

Geriatric Patients

Population pharmacokinetic analysis in HIV-infected subjects showed that etravirine pharmacokinetics are not considerably different within the age range (18 to 77 years) evaluated [see Use in Specific Populations (8.5)] .

Pediatric Patients

The pharmacokinetics of etravirine in 115 treatment-experienced HIV-1-infected pediatric subjects, 2 years to less than 18 years of age showed that the administered weight-based dosages resulted in etravirine exposure comparable to that in adults receiving Etravirine 200 mg twice daily [see Dosage and Administration (2.3)] . The pharmacokinetic parameters for etravirine (AUC12hand C0h) are summarized in Table 6.

Table 6: Pharmacokinetic Parameters for Etravirine in Treatment-Experienced HIV-1-Infected Pediatric Subjects 2 Years to Less Than 18 Years of Age (TMC125-C213 [Population PK] and TMC125-C234/P1090)
Study | TMC125-C213 | TMC125-C234/ IMPAACT P1090
Age Range (years) | (6 years to less than 18 years) | (2 years to less than 6 years)
Parameter | N=101 | N=14
AUC12h(ng∙h/mL)
Geometric mean ± standard deviation | 3742 ± 4314 | 3504 ± 2923
Median (range) | 4499 (62–28865) | 3579 (1221–11815)
C0h(ng/mL)
Geometric mean ± standard deviation | 205 ± 342 | 183 ± 240
Median (range) | 287 (2–2276) | 162 (54–908)

The pharmacokinetics and dose of etravirine in pediatric subjects less than 2 years of age have not been established [see Use in Specific Populations (8.4)].

Male and Female Patients

No significant pharmacokinetic differences have been observed between males and females.

Racial or Ethnic Groups

Population pharmacokinetic analysis of etravirine in HIV-infected subjects did not show an effect of race on exposure to etravirine.

Patients with Renal Impairment

The pharmacokinetics of etravirine have not been studied in patients with renal impairment. The results from a mass balance study with^14C-etravirine showed that less than 1.2% of the administered dose of etravirine is excreted in the urine as metabolites. No unchanged drug was detected in the urine. As etravirine is highly bound to plasma proteins, it is unlikely that it will be significantly removed by hemodialysis or peritoneal dialysis [see Use in Specific Populations (8.7)] .

Patients with Hepatic Impairment

Etravirine is primarily metabolized by the liver. The steady state pharmacokinetic parameters of etravirine were similar after multiple dose administration of Etravirine to subjects with normal hepatic function (16 subjects), mild hepatic impairment (Child-Pugh Class A, 8 subjects), and moderate hepatic impairment (Child-Pugh Class B, 8 subjects). The effect of severe hepatic impairment on the pharmacokinetics of etravirine has not been evaluated [see Use in Specific Populations (8.6)] .

Pregnancy and Postpartum

After intake of Etravirine 200 mg twice daily in combination with other antiretroviral agents (13 subjects with 2 NRTIs, 1 subject with 2 NRTIs + lopinavir + ritonavir, 1 subject with 2 NRTIs + raltegravir), based on intra-individual comparison, the Cmaxand AUC12hof total etravirine were 23 to 42% higher during pregnancy compared with postpartum (6–12 weeks). The Cminof total etravirine was 78 to 125% higher during pregnancy compared with postpartum (6–12 weeks), while two subjects had Cmin<10 ng/mL in the postpartum period (6–12 weeks) [Cminof total etravirine was 11 to 16% higher when these 2 subjects are excluded] (see Table 7) [see Use in Specific Populations (8.1)] . Increased etravirine exposures during pregnancy are not considered clinically significant. The protein binding of etravirine was similar (>99%) during the second trimester, third trimester, and postpartum period.

Table 7: Pharmacokinetic Results of Total Etravirine After Administration of Etravirine 200 mg Twice Daily as Part of an Antiretroviral Regimen, During the 2ndTrimester of Pregnancy, the 3rdTrimester of Pregnancy, and Postpartum.
Parameter Mean ± SD (median) | Postpartum N=10 | 2ndTrimester N=13 | 3rdTrimester N=10 [n=9 for AUC 12h]
Cmin, ng/mL | 269 ± 182 (284) [Two subjects had C min <10 ng/mL, C min was 334 ± 135 (315) in the postpartum period when these subjects were excluded from the descriptive analysis (N=8).] | 383 ± 210 (346) | 349 ± 103 (371)
Cmax, ng/mL | 569 ± 261 (528) | 774 ± 300 (828) | 785 ± 238 (694)
AUC12h, ng∙h/mL | 5004 ± 2521 (5246) | 6617 ± 2766 (6836) | 6846 ± 1482 (6028)

Patients with Hepatitis B and/or Hepatitis C Virus Co-Infection

Population pharmacokinetic analysis of the TMC125-C206 and TMC125-C216 trials showed reduced clearance for etravirine in HIV-1-infected subjects with hepatitis B and/or C virus co-infection. Based upon the safety profile of Etravirine [see Adverse Reactions (6)] , no dose adjustment is necessary in patients co-infected with hepatitis B and/or C virus.

Drug Interactions

Etravirine is a substrate of CYP3A, CYP2C9, and CYP2C19. Therefore, co-administration of Etravirine with drugs that induce or inhibit CYP3A, CYP2C9, and CYP2C19 may alter the therapeutic effect or adverse reaction profile of Etravirine.

Etravirine is an inducer of CYP3A and inhibitor of CYP2C9, CYP2C19 and P-gp. Therefore, co-administration of drugs that are substrates of CYP3A, CYP2C9 and CYP2C19 or are transported by P-gp with Etravirine may alter the therapeutic effect or adverse reaction profile of the co-administered drug(s).

Drug interaction studies were performed with Etravirine and other drugs likely to be co-administered and some drugs commonly used as probes for pharmacokinetic interactions. The effects of co-administration of other drugs on the AUC, Cmax, and Cminvalues of etravirine are summarized in Table 8 (effect of other drugs on Etravirine). The effect of co-administration of Etravirine on the AUC, Cmax, and Cminvalues of other drugs are summarized in Table 9 (effect of Etravirine on other drugs). For information regarding clinical recommendations, [see Drug Interactions (7)] .

Table 8: Drug Interactions: Pharmacokinetic Parameters for Etravirine in the Presence of Co-administered Drugs
Co-administered Drug | Dose/Schedule of Co-administered Drug | N | Exposure | Mean Ratio of Etravirine Pharmacokinetic Parameters 90% CI; No Effect = 1.00
Co-administered Drug | Dose/Schedule of Co-administered Drug | N | Exposure | Cmax | AUC | Cmin
Co-administration with HIV protease inhibitors (PIs)
Atazanavir | 400 mg once daily | 14 | ↑ | 1.47 (1.36–1.59) | 1.50 (1.41–1.59) | 1.58 (1.46–1.70)
Atazanavir/ ritonavir [The systemic exposure of etravirine when co-administered with atazanavir/ritonavir in HIV infected subjects is similar to exposures of etravirine observed in the Phase 3 trials after co-administration of Etravirine and darunavir/ritonavir (as part of the background regimen).] | 300/100 mg once daily | 14 | ↑ | 1.30 (1.17–1.44) | 1.30 (1.18–1.44) | 1.26 (1.12–1.42)
Darunavir/ ritonavir | 600/100 mg twice daily | 14 | ↓ | 0.68 (0.57–0.82) | 0.63 (0.54–0.73) | 0.51 (0.44–0.61)
Lopinavir/ ritonavir (tablet) | 400/100 mg twice daily | 16 | ↓ | 0.70 (0.64–0.78) | 0.65 (0.59–0.71) | 0.55 (0.49–0.62)
Ritonavir | 600 mg twice daily | 1 1 | ↓ | 0.68 (0.55–0.85) | 0.54 (0.41–0.73) | N.A.
Saquinavir/ ritonavir | 1000/100 mg twice daily | 1 4 | ↓ | 0.63 (0.53–0.75) | 0.67 (0.56–0.80) | 0.71 (0.58–0.87)
Tipranavir/ ritonavir | 500/200 mg twice daily | 1 9 | ↓ | 0.29 (0.22–0.40) | 0.24 (0.18–0.33) | 0.18 (0.13–0.25)
Co-administration with nucleoside reverse transcriptase inhibitors (NRTIs)
Didanosine | 400 mg once daily | 15 | ↔ | 1.16 (1.02–1.32) | 1.11 (0.99–1.25) | 1.05 (0.93–1.18)
Tenofovir disoproxil fumarate | 300 mg once daily | 23 | ↓ | 0.81 (0.75–0.88) | 0.81 (0.75–0.88) | 0.82 (0.73–0.91)
Co-administration with CCR5 antagonists
Maraviroc | 300 mg twice daily | 14 | ↔ | 1.05 (0.95–1.17) | 1.06 (0.99–1.14) | 1.08 (0.98–1.19)
Maraviroc (when co-administered with darunavir/ ritonavir) [The reference for etravirine exposure is the pharmacokinetic parameters of etravirine in the presence of darunavir/ritonavir.] | 150/600/100 mg twice daily | 10 | ↔ | 1.08 (0.98–1.20) | 1.00 (0.86–1.15) | 0.81 (0.65–1.01)
Co-administration with integrase strand transfer inhibitors
Raltegravir | 400 mg twice daily | 19 | ↔ | 1.04 (0.97–1.12) | 1.10 (1.03–1.16) | 1.17 (1.10–1.26)
Co-administration with other drugs
Artemether/ lumefantrine | 80/480 mg, 6 doses at 0, 8, 24, 36, 48, and 60 hours | 14 | ↔ | 1.11 (1.06–1.17) | 1.10 (1.06–1.15) | 1.08 (1.04–1.14)
Atorvastatin | 40 mg once daily | 16 | ↔ | 0.97 (0.93–1.02) | 1.02 (0.97–1.07) | 1.10 (1.02–1.19)
Clarithromycin | 500 mg twice daily | 15 | ↑ | 1.46 (1.38–1.56) | 1.42 (1.34–1.50) | 1.46 (1.36–1.58)
Fluconazole | 200 mg once daily in the morning | 16 | ↑ | 1.75 (1.60–1.91) | 1.86 (1.73–2.00) | 2.09 (1.90–2.31)
Omeprazole | 40 mg once daily | 18 | ↑ | 1.17 (0.96–1.43) | 1.41 (1.22–1.62) | N.A.
Paroxetine | 20 mg once daily | 16 | ↔ | 1.05 (0.96–1.15) | 1.01 (0.93–1.10) | 1.07 (0.98–1.17)
Ranitidine | 150 mg twice daily | 18 | ↓ | 0.94 (0.75–1.17) | 0.86 (0.76–0.97) | N.A.
Rifabutin | 300 mg once daily | 12 | ↓ | 0.63 (0.53–0.74) | 0.63 (0.54–0.74) | 0.65 (0.56–0.74)
Voriconazole | 200 mg twice daily | 16 | ↑ | 1.26 (1.16–1.38) | 1.36 (1.25–1.47) | 1.52 (1.41–1.64)
CI = Confidence Interval; N = number of subjects with data; N.A. = not available; ↑ = increase; ↓ = decrease; ↔ = no change

Table 9: Drug Interactions: Pharmacokinetic Parameters for Co-administered Drugs in the Presence of Etravirine
Co-administered Drug | Dose/Schedule of Co-administered Drug | N | Exposure | Mean Ratio of Co-administered Drug Pharmacokinetic Parameters 90% CI; No effect = 1.00
Co-administered Drug | Dose/Schedule of Co-administered Drug | N | Exposure | Cmax | AUC | Cmin
Co-administration with HIV protease inhibitors (PIs)
Atazanavir | 400 mg once daily | 14 | ↓ | 0.97 (0.73–1.29) | 0.83 (0.63–1.09) | 0.53 (0.38–0.73)
Atazanavir/ ritonavir | 300/100 mg once daily | 13 | ↓ | 0.97 (0.89–1.05) | 0.86 (0.79–0.93) | 0.62 (0.55–0.71)
Atazanavir/ ritonavir [HIV-infected subjects] | 300/100 mg once daily | 20 | ↓ | 0.96 (0.80–1.16) | 0.96 (0.76–1.22) | 0.82 (0.55–1.22)
Darunavir/ ritonavir | 600/100 mg twice daily | 15 | ↔ | 1.11 (1.01–1.22) | 1.15 (1.05–1.26) | 1.02 (0.90–1.17)
Fosamprenavir/ ritonavir | 700/100 mg twice daily | 8 | ↑ | 1.62 (1.47–1.79) | 1.69 (1.53–1.86) | 1.77 (1.39–2.25)
Lopinavir/ ritonavir (tablet) | 400/100 mg twice daily | 16 | ↔ | 0.89 (0.82–0.96) | 0.87 (0.83–0.92) | 0.80 (0.73–0.88)
Saquinavir/ ritonavir | 1000/100 mg twice daily | 15 | ↔ | 1.00 (0.70–1.42) | 0.95 (0.64–1.42) | 0.80 (0.46–1.38)
Tipranavir/ ritonavir | 500/200 mg twice daily | 19 | ↑ | 1.14 (1.02–1.27) | 1.18 (1.03–1.36) | 1.24 (0.96–1.59)
Co-administration with nucleoside reverse transcriptase inhibitors (NRTIs)
Didanosine | 400 mg once daily | 14 | ↔ | 0.91 (0.58–1.42) | 0.99 (0.79–1.25) | N.A.
Tenofovir disoproxil fumarate | 300 mg once daily | 19 | ↔ | 1.15 (1.04–1.27) | 1.15 (1.09–1.21) | 1.19 (1.13–1.26)
Co-administration with CCR5 antagonists
Maraviroc | 300 mg twice daily | 14 | ↓ | 0.40 (0.28–0.57) | 0.47 (0.38–0.58) | 0.61 (0.53–0.71)
Maraviroc (when co-administered with darunavir/ ritonavir) [compared to maraviroc 150 mg twice daily] | 150/600/100 mg twice daily | 10 | ↑ | 1.77 (1.20–2.60) | 3.10 (2.57–3.74) | 5.27 (4.51–6.15)
Co-administration with integrase strand transfer inhibitors
Dolutegravir | 50 mg once daily | 16 | ↓ | 0.48 (0.43 to 0.54) | 0.29 (0.26 to 0.34) | 0.12 (0.09 to 0.16)
Dolutegravir (when co-administered with darunavir/ritonavir) | 50 mg once daily + 600/100 mg twice daily | 9 | ↓ | 0.88 (0.78 to 1.00) | 0.75 (0.69 to 0.81) | 0.63 (0.52 to 0.76)
Dolutegravir (when co-administered with lopinavir/ritonavir | 50 mg once daily + 400/100 mg twice daily | 8 | ↔ | 1.07 (1.02 to 1.13) | 1.11 (1.02 to 1.20) | 1.28 (1.13 to 1.45)
Raltegravir | 400 mg twice daily | 19 | ↓ | 0.89 (0.68–1.15) | 0.90 (0.68–1.18) | 0.66 (0.34–1.26)
Co-administration with other drugs
Artemether | 80/480 mg, 6 doses at 0, 8, 24, 36, 48, and 60 hours | 15 | ↓ | 0.72 (0.55–0.94) | 0.62 (0.48–0.80) | 0.82 (0.67–1.01)
Dihydroartemisinin |  | 15 | ↓ | 0.84 (0.71–0.99) | 0.85 (0.75–0.97) | 0.83 (0.71–0.97)
Lumefantrine |  | 15 | ↓ | 1.07 (0.94–1.23) | 0.87 (0.77–0.98) | 0.97 (0.83–1.15)
Atorvastatin | 40 mg once daily | 16 | ↓ | 1.04 (0.84–1.30) | 0.63 (0.58–0.68) | N.A.
2-hydroxy-atorvastatin |  | 16 | ↑ | 1.76 (1.60–1.94) | 1.27 (1.19–1.36) | N.A.
Buprenorphine | Individual dose regimen ranging from 4/1 mg to 16/4 mg once daily | 16 | ↓ | 0.89 (0.76–1.05) | 0.75 (0.66–0.84) | 0.60 (0.52–0.68)
Norbuprenorphine |  | 16 | ↔ | 1.08 (0.95–1.23) | 0.88 (0.81–0.96) | 0.76 (0.67–0.87)
Clarithromycin | 500 mg twice daily | 15 | ↓ | 0.66 (0.57–0.77) | 0.61 (0.53–0.69) | 0.47 (0.38–0.57)
14-hydroxy-clarithromycin |  | 15 | ↑ | 1.33 (1.13–1.56) | 1.21 (1.05–1.39) | 1.05 (0.90–1.22)
Digoxin | 0.5 mg single dose | 16 | ↑ | 1.19 (0.96–1.49) | 1.18 (0.90–1.56) | N.A.
Ethinylestradiol | 0.035 mg once daily | 16 | ↑ | 1.33 (1.21–1.46) | 1.22 (1.13–1.31) | 1.09 (1.01–1.18)
Norethindrone | 1 mg once daily | 16 | ↔ | 1.05 (0.98–1.12) | 0.95 (0.90–0.99) | 0.78 (0.68–0.90)
Fluconazole | 200 mg once daily in the morning | 15 | ↔ | 0.92 (0.85–1.00) | 0.94 (0.88–1.01) | 0.91 (0.84–0.98)
R(-) Methadone | Individual dose regimen ranging from 60 to 130 mg/day | 16 | ↔ | 1.02 (0.96–1.09) | 1.06 (0.99–1.13) | 1.10 (1.02–1.19)
S(+) Methadone |  | 16 | ↔ | 0.89 (0.83–0.97) | 0.89 (0.82–0.96) | 0.89 (0.81–0.98)
Paroxetine | 20 mg once daily | 16 | ↔ | 1.06 (0.95–1.20) | 1.03 (0.90–1.18) | 0.87 (0.75–1.02)
Rifabutin | 300 mg once daily | 12 | ↓ | 0.90 (0.78–1.03) | 0.83 (0.75–0.94) | 0.76 (0.66–0.87)
25- O-desacetylrifabutin | 300 mg once daily | 12 | ↓ | 0.85 (0.72–1.00) | 0.83 (0.74–0.92) | 0.78 (0.70–0.87)
Sildenafil | 50 mg single dose | 15 | ↓ | 0.55 (0.40–0.75) | 0.43 (0.36–0.51) | N.A.
N-desmethyl-sildenafil |  | 15 | ↓ | 0.75 (0.59–0.96) | 0.59 (0.52–0.68) | N.A.
Voriconazole | 200 mg twice daily | 14 | ↑ | 0.95 (0.75–1.21) | 1.14 (0.88–1.47) | 1.23 (0.87–1.75)
CI = Confidence Interval; N = number of subjects with data; N.A. = not available; ↑ = increase; ↓ = decrease; ↔ = no change

12.4 Microbiology

Mechanism of Action

Etravirine is an NNRTI of HIV-1. Etravirine binds directly to reverse transcriptase (RT) and blocks the RNA-dependent and DNA-dependent DNA polymerase activities by causing a disruption of the enzyme's catalytic site. Etravirine does not inhibit the human DNA polymerases α, β, and γ.

Antiviral Activity in Cell Culture

Etravirine exhibited activity against laboratory strains and clinical isolates of wild-type HIV-1 in acutely infected T-cell lines, human peripheral blood mononuclear cells, and human monocytes/macrophages with median EC50values ranging from 0.9 to 5.5 nM (i.e., 0.4 to 2.4 ng/mL). Etravirine demonstrated antiviral activity in cell culture against a broad panel of HIV-1 group M isolates (subtype A, B, C, D, E, F, G) with EC50values ranging from 0.29 to 1.65 nM and EC50values ranging from 11.5 to 21.7 nM against group O primary isolates. Etravirine did not show antagonism when studied in combination with the following antiretroviral drugs—the NNRTIs delavirdine, efavirenz, and nevirapine; the N(t)RTIs abacavir, didanosine, emtricitabine, lamivudine, stavudine, tenofovir, and zidovudine; the PIs amprenavir, atazanavir, darunavir, indinavir, lopinavir, nelfinavir, ritonavir, saquinavir, and tipranavir; the gp41 fusion inhibitor ENF; the integrase strand transfer inhibitor raltegravir and the CCR5 co-receptor antagonist maraviroc.

Resistance

In Cell Culture

Etravirine-resistant strains were selected in cell culture originating from wild-type HIV-1 of different origins and subtypes, as well as NNRTI resistant HIV-1. Development of reduced susceptibility to etravirine typically required more than one substitution in reverse transcriptase of which the following were observed most frequently: L100I, E138K, E138G, V179I, Y181C, and M230I.

In Treatment-Experienced Subjects

In the Phase 3 trials TMC125-C206 and TMC125-C216, substitutions that developed most commonly in subjects with virologic failure at Week 48 to the Etravirine-containing regimen were V179F, V179I, and Y181C which usually emerged in a background of multiple other NNRTI resistance-associated substitutions. In all the trials conducted with Etravirine in HIV-1 infected subjects, the following substitutions emerged most commonly: L100I, E138G, V179F, V179I, Y181C and H221Y. Other NNRTI-resistance-associated substitutions which emerged on etravirine treatment in less than 10% of the virologic failure isolates included K101E/H/P, K103N/R, V106I/M, V108I, Y181I, Y188L, V189I, G190S/C, N348I and R356K. The emergence of NNRTI substitutions on etravirine treatment contributed to decreased susceptibility to etravirine with a median fold-change in etravirine susceptibility of 40-fold from reference and a median fold-change of 6-fold from baseline.

Cross-Resistance

Cross-resistance among NNRTIs has been observed. Cross-resistance to delavirdine, efavirenz, and/or nevirapine is expected after virologic failure with an etravirine-containing regimen. Virologic failure on a rilpivirine-containing regimen with development of rilpivirine resistance is likely to result in cross-resistance to etravirine (see Treatment-Naïve HIV-1-Infected Subjects in the Phase 3 Trials for EDURANT (rilpivirine)below). Cross-resistance to etravirine has been observed after virologic failure on a doravirine-containing regimen with development of doravirine resistance. Some NNRTI-resistant viruses are susceptible to etravirine, but genotypic and phenotypic testing should guide the use of etravirine (see Baseline Genotype/Phenotype and Virologic Outcome Analysesbelow).

Site-Directed NNRTI Mutant Virus

Etravirine showed antiviral activity against 55 of 65 HIV-1 strains (85%) with single amino acid substitutions at RT positions associated with NNRTI resistance, including the most commonly found K103N. The single amino acid substitutions associated with an etravirine reduction in susceptibility greater than 3-fold were K101A, K101P, K101Q, E138G, E138Q, Y181C, Y181I, Y181T, Y181V, and M230L, and of these, the greatest reductions were Y181I (13-fold change in EC50value) and Y181V (17-fold change in EC50value). Mutant strains containing a single NNRTI resistance-associated substitution (K101P, K101Q, E138Q, or M230L) had cross-resistance between etravirine and efavirenz. The majority (39 of 61; 64%) of the NNRTI mutant viruses with 2 or 3 amino acid substitutions associated with NNRTI resistance had decreased susceptibility to etravirine (fold-change greater than 3). The highest levels of resistance to etravirine were observed for HIV-1 harboring a combination of substitutions V179F + Y181C (187 fold-change), V179F + Y181I (123 fold-change), or V179F + Y181C + F227C (888 fold-change).

Clinical Isolates

Etravirine retained a fold-change less than or equal to 3 against 60% of 6171 NNRTI-resistant clinical isolates. In the same panel, the proportion of clinical isolates resistant to delavirdine, efavirenz and/or nevirapine (defined as a fold-change above their respective biological cutoff values in the assay) was 79%, 87%, and 95%, respectively. In TMC125-C206 and TMC125-C216, 34% of the baseline isolates had decreased susceptibility to etravirine (fold-change greater than 3) and 60%, 69%, and 78% of all baseline isolates were resistant to delavirdine, efavirenz, and nevirapine, respectively. Of subjects who received etravirine and were virologic failures in TMC125-C206 and TMC125-C216, 90%, 84%, and 96% of viral isolates obtained at the time of treatment failure were resistant to delavirdine, efavirenz, and nevirapine, respectively.

Treatment-Naïve HIV-1-Infected Subjects in the Phase 3 Trials for EDURANT (Rilpivirine)

There are currently no clinical data available on the use of etravirine in subjects who experienced virologic failure on a rilpivirine-containing regimen. However, in the rilpivirine adult clinical development program, there was evidence of phenotypic cross-resistance between rilpivirine and etravirine. In the pooled analyses of the Phase 3 clinical trials for rilpivirine, 38 rilpivirine virologic failure subjects had evidence of HIV-1 strains with genotypic and phenotypic resistance to rilpivirine. Of these subjects, 89% (34 subjects) of virologic failure isolates were cross-resistant to etravirine based on phenotype data. Consequently, it can be inferred that cross-resistance to etravirine is likely after virologic failure and development of rilpivirine resistance. Refer to the prescribing information for EDURANT (rilpivirine) for further information.

Baseline Genotype/Phenotype and Virologic Outcome Analyses

In TMC125-C206 and TMC125-C216, the presence at baseline of the substitutions L100I, E138A, I167V, V179D, V179F, Y181I, Y181V, or G190S was associated with a decreased virologic response to etravirine. Additional substitutions associated with a decreased virologic response to etravirine when in the presence of 3 or more additional 2008 IAS-USA defined NNRTI substitutions include A98G, K101H, K103R, V106I, V179T, and Y181C. The presence of K103N, which was the most prevalent NNRTI substitution in TMC125-C206 and TMC125-C216 at baseline, did not affect the response in the Etravirine arm. Overall, response rates to etravirine decreased as the number of baseline NNRTI substitutions increased (shown as the proportion of subjects achieving viral load less than 50 plasma HIV RNA copies/mL at Week 48) (Table 10).

Table 10: Proportion of Subjects With Less Than 50 HIV-1 RNA Copies/mL at Week 48 by Baseline Number of IAS-USA-Defined NNRTI Substitutions in the Non-VF Excluded Population of the Pooled TMC125-C206 and TMC125-C216
# IAS-USA-Defined NNRTI substitutions [2008 IAS-USA defined substitutions = V90I, A98G, L100I, K101E/H/P, K103N, V106A/I/M, V108I, E138A, V179D/F/T, Y181C/I/V, Y188C/H/L, G190A/S, P225H, M230L] | Etravirine N=561
# IAS-USA-Defined NNRTI substitutions [2008 IAS-USA defined substitutions = V90I, A98G, L100I, K101E/H/P, K103N, V106A/I/M, V108I, E138A, V179D/F/T, Y181C/I/V, Y188C/H/L, G190A/S, P225H, M230L] | Re-used/not used ENF | de novoENF
All ranges | 61% (254/418) | 76% (109/143)
0 | 68% (52/76) | 95% (20/21)
1 | 67% (72/107) | 77% (24/31)
2 | 64% (75/118) | 86% (38/44)
3 | 55% (36/65) | 62% (16/26)
≥ 4 | 37% (19/52) | 52% (11/21)
 | Placebo N=592
All ranges | 34% (147/435) | 59% (93/157)
ENF: enfuvirtide

Response rates assessed by baseline etravirine phenotype are shown in Table 11. These baseline phenotype groups are based on the select subject populations in TMC125-C206 and TMC125-C216 and are not meant to represent definitive clinical susceptibility breakpoints for Etravirine. The data are provided to give clinicians information on the likelihood of virologic success based on pre-treatment susceptibility to etravirine in treatment-experienced patients.

Table 11: Proportion of Subjects With Less Than 50 HIV-1 RNA Copies/mL at Week 48 by Baseline Phenotype and ENF Use in the Pooled TMC125-C206 and TMC125-C216 [Non-VF excluded analysis]
Fold Change | Etravirine N=559
Fold Change | Re-used/not used ENF | de novoENF | Clinical response range
All ranges | 61% (253/416) | 76% (109/143) | Overall Response
0–3 | 69% (188/274) | 83% (75/90) | Higher than Overall Response
> 3–13 | 50% (39/78) | 66% (25/38) | Lower than Overall Response
> 13 | 41% (26/64) | 60% (9/15) | Lower than Overall Response
 | Placebo N=583
All ranges | 34% (145/429) | 60% (92/154)
ENF: enfuvirtide

The proportion of virologic responders (viral load less than 50 HIV-1 RNA copies/mL) by the phenotypic susceptibility score (PSS) of the background therapy, including ENF, is shown in Table 12.

Table 12: Virologic Response (Viral Load Less Than 50 HIV-1 RNA Copies/mL) at Week 48 by Phenotypic Susceptibility Score (PSS) in the Non-VF Excluded Population of TMC125-C206 and TMC125-C216
PSS [The phenotypic susceptibility score (PSS) was defined as the total number of active antiretroviral drugs in the background therapy to which a subject's baseline viral isolate showed sensitivity in phenotypic resistance tests. Each drug in the background therapy was scored as a '1' or '0' based on whether the viral isolate was considered susceptible or resistant to that drug, respectively. In the calculation of the PSS, darunavir was counted as a sensitive antiretroviral if the FC was less than or equal to 10; ENF was counted as a sensitive antiretroviral if it had not been used previously. Etravirine was not included in this calculation.] | Etravirine + BR N=559 | Placebo + BR N=586
0 | 43% (40/93) | 5% (5/95)
1 | 61% (125/206) | 28% (64/226)
2 | 77% (114/149) | 59% (97/165)
≥ 3 | 75% (83/111) | 72% (72/100)

13 NONCLINICAL TOXICOLOGY

13.1 Carcinogenesis, Mutagenesis, Impairment of Fertility

Carcinogenesis

Etravirine was evaluated for carcinogenic potential by oral gavage administration to mice and rats for up to approximately 104 weeks. Daily doses of 50, 200 and 400 mg/kg were administered to mice and doses of 70, 200 and 600 mg/kg were administered to rats in the initial period of approximately 41 to 52 weeks. The high and middle doses were subsequently adjusted due to tolerability and reduced by 50% in mice and by 50 to 66% in rats to allow for completion of the studies. In the mouse study, statistically significant increases in the incidences of hepatocellular carcinoma and incidences of hepatocellular adenomas or carcinomas combined were observed in treated females. In the rat study, no statistically significant increases in tumor findings were observed in either sex. The relevance of these liver tumor findings in mice to humans is not known. Because of tolerability of the formulation in these rodent studies, maximum systemic drug exposures achieved at the doses tested were lower than those in humans at the clinical dose (400 mg/day), with animal vs. human AUC ratios being 0.6-fold (mice) and 0.2-to-0.7-fold (rats).

Mutagenesis

Etravirine tested negative in the in vitroAmes reverse mutation assay, in vitrochromosomal aberration assay in human lymphocyte, and in vitroclastogenicity mouse lymphoma assay, tested in the absence and presence of a metabolic activation system. Etravirine did not induce chromosomal damage in the in vivomicronucleus test in mice.

Impairment of Fertility

No effects on fertility and early embryonic development were observed when etravirine was tested in rats at maternal doses up to 500 mg/day, resulting in systemic drug exposure up to the recommended human dose (400 mg/day).

14 CLINICAL STUDIES

14.1 Treatment-Experienced Adult Subjects

The clinical efficacy of Etravirine is derived from the analyses of 48-week data from 2 ongoing, randomized, double-blinded, placebo-controlled, Phase 3 trials, TMC125-C206 and TMC125-C216 (DUET-1 and DUET-2) in subjects with 1 or more NNRTI resistance-associated substitutions. These trials are identical in design and the results below are pooled data from the two trials.

TMC125-C206 and TMC125-C216 are Phase 3 studies designed to evaluate the safety and antiretroviral activity of Etravirine in combination with a background regimen (BR) as compared to placebo in combination with a BR. Eligible subjects were treatment-experienced HIV-1-infected subjects with plasma HIV-1 RNA greater than 5000 copies/mL while on an antiretroviral regimen for at least 8 weeks. In addition, subjects had 1 or more NNRTI resistance-associated substitutions at screening or from prior genotypic analysis, and 3 or more of the following primary PI substitutions at screening: D30N, V32I, L33F, M46I/L, I47A/V, G48V, I50L/V, V82A/F/L/S/T, I84V, N88S, or L90M. Randomization was stratified by the intended use of ENF in the BR, previous use of darunavir/ritonavir, and screening viral load. Virologic response was defined as HIV-1 RNA less than 50 copies/mL at Week 48.

All study subjects received darunavir/ritonavir as part of their BR, and at least 2 other investigator-selected antiretroviral drugs (N[t]RTIs with or without ENF). Of Etravirine-treated subjects, 25.5% used ENF for the first time (de novo) and 20.0% re-used ENF. Of placebo-treated subjects, 26.5% used de novoENF and 20.4% re-used ENF.

In the pooled analysis for TMC125-C206 and TMC125-C216, demographics and baseline characteristics were balanced between the Etravirine arm and the placebo arm (Table 13). Table 13 displays selected demographic and baseline disease characteristics of the subjects in the Etravirine and placebo arms.

Table 13: Demographic and Baseline Disease Characteristics of Subjects(Pooled Analysis TMC125-C206 and TMC125-C216)--
 | Etravirine + BR N=599 | Placebo + BR N=604
Demographic characteristics
Median age, years (range) | 46 (18–77) | 45 (18–72)
Sex
Male | 90.0% | 88.6%
Female | 10.0% | 11.4%
Race
White | 70.1% | 69.8%
Black | 13.2% | 13.0%
Hispanic | 11.3% | 12.2%
Asian | 1.3% | 0.6%
Other | 4.1% | 4.5%
Baseline disease characteristics
Median baseline plasma HIV-1 RNA (range), log10copies/mL | 4.8 (2.7–6.8) | 4.8 (2.2–6.5)
Percentage of subjects with baseline viral load:
< 30,000 copies/mL | 27.5% | 28.8%
≥ 30,000 copies/mL and < 100,000 copies/mL | 34.4% | 35.3%
≥ 100,000 copies/mL | 38.1% | 35.9%
Median baseline CD4+ cell count (range), cells/mm^3 | 99 (1–789) | 109 (0–912)
Percentage of subjects with baseline CD4+ cell count:
< 50 cells/mm^3 | 35.6% | 34.7%
≥ 50 cells/mm^3and < 200 cells/mm^3 | 34.8% | 34.5%
≥ 200 cells/mm^3 | 29.6% | 30.8%
Median (range) number of primary PI substitutions [IAS-USA primary PI substitutions [August/September 2007]: D30N, V32I, L33F, M46I/L, I47A/V, G48V, I50L/V, I54L/M, L76V, V82A/F/L/S/T, I84V, N88S, L90M] | 4 (0–7) | 4 (0–8)
Percentage of subjects with previous use of NNRTIs:
0 | 8.2% | 7.9%
1 | 46.9% | 46.7%
> 1 | 44.9% | 45.4%
Percentage of subjects with previous use of the following NNRTIs: | 70.3% | 72.5%
Efavirenz | 57.1% | 58.6%
Nevirapine | 13.7% | 12.6%
Delavirdine
Median (range) number of NNRTI RASs [Tibotec NNRTI RASs [June 2008]: A98G, V90I, L100I, K101E/H/P/Q, K103H/N/S/T, V106A/M/I, V108I, E138A/G/K/Q, V179D/E/F/G/I/T, Y181C/I/V, Y188C/H/L, V189I, G190A/C/E/Q/S, H221Y, P255H, F227C/L, M230I/L, P236L, K238N/T, Y318F] | 2 (0–8) | 2 (0–7)
Median fold change of the virus for the following NNRTIs:
Delavirdine | 27.3 | 26.1
Efavirenz | 63.9 | 45.4
Etravirine | 1.6 | 1.5
Nevirapine | 74.3 | 74.0
Percentage of subjects with previous use of a fusion inhibitor | 39.6% | 42.2%
Percentage of subjects with a Phenotypic Sensitivity Score (PSS) for the background therapy [The PSS was calculated for the background therapy (as determined on Day 7). Percentages are based on the number of subjects with available phenotype data. For fusion inhibitors (enfuvirtide), subjects were considered resistant if the drug was used in previous therapy up to baseline. Etravirine is not included in this calculation.] of:
0 | 17.0% | 16.2%
1 | 36.5% | 38.7%
2 | 26.9% | 27.8%
≥ 3 | 19.7% | 17.3%
RASs = Resistance-Associated Substitutions, BR=background regimen, FC = fold change in EC50

Efficacy at Week 48 for subjects in the Etravirine and placebo arms for the pooled TMC125-C206 and TMC125-C216 study populations are shown in Table 14.

Table 14: Treatment Outcomes at Week 48 (Pooled Analysis TMC125-C206 and TMC125-C216)
 | Etravirine + BR N=599 | Placebo + BR N=604
Virologic responders at Week 48 Viral Load < 50 HIV-1 RNA copies/mL | 359 (60%) | 232 (38%)
Virologic failures at Week 48 Viral Load ≥ 50 HIV-1 RNA copies/mL | 123 (21%) | 201 (33%)
Death | 11 (2%) | 19 (3%)
Discontinuations before Week 48:
due to virologic failures | 58 (10%) | 110 (18%)
due to adverse events | 31 (5%) | 14 (2%)
due to other reasons | 17 (3%) | 28 (5%)
BR=background regimen

At Week 48, 70.8% of Etravirine-treated subjects achieved HIV-1 RNA less than 400 copies/mL as compared to 46.4% of placebo-treated subjects. The mean decrease in plasma HIV-1 RNA from baseline to Week 48 was -2.23 log10copies/mL for Etravirine-treated subjects and -1.46 log10copies/mL for placebo-treated subjects. The mean CD4+ cell count increase from baseline for Etravirine-treated subjects was 96 cells/mm^3and 68 cells/mm^3for placebo-treated subjects.

Of the study population who either re-used or did not use ENF, 57.4% of Etravirine-treated subjects and 31.7% of placebo-treated subjects achieved HIV-1 RNA less than 50 copies/mL. Of the study population using ENF de novo,67.3% of Etravirine-treated subjects and 57.2% of placebo-treated subjects achieved HIV-1 RNA less than 50 copies/mL.

Treatment-emergent CDC category C events occurred in 4% of Etravirine-treated subjects and 8.4% of placebo-treated subjects.

Study TMC125-C227 was a randomized, exploratory, active-controlled, open-label, Phase 2b trial. Eligible subjects were treatment-experienced, PI-naïve HIV-1-infected subjects with genotypic evidence of NNRTI resistance at screening or from prior genotypic analysis. The virologic response was evaluated in 116 subjects who were randomized to Etravirine (59 subjects) or an investigator-selected PI (57 subjects), each given with 2 investigator-selected N(t)RTIs. Etravirine-treated subjects had lower antiviral responses associated with reduced susceptibility to the N(t)RTIs and to Etravirine as compared to the control PI-treated subjects.

14.2 Treatment-Experienced Pediatric Subjects (2 Years to Less Than 18 Years of Age)

The efficacy of Etravirine for treatment-experienced pediatric subjects is based on two Phase 2 trials, TMC125-C213 and TMC125-C234/IMPAACT P1090.

Pediatric Subjects (6 Years to Less Than 18 Years of Age [TMC125-C213])

TMC125-C213, a single-arm, Phase 2 trial evaluating the pharmacokinetics, safety, tolerability, and efficacy of Etravirine enrolled 101 antiretroviral treatment-experienced HIV-1 infected pediatric subjects 6 years to less than 18 years of age and weighing at least 16 kg. Subjects eligible for this trial were on an antiretroviral regimen with confirmed plasma HIV-1 RNA of at least 500 copies/mL and viral susceptibility to Etravirine at screening.

The median baseline plasma HIV-1 RNA was 3.9 log10copies/mL, and the median baseline CD4+ cell count was 385 × 10^6cells/mm^3.

At Week 24, 52% of subjects had HIV-1 RNA less than 50 copies per mL. The proportion of subjects with HIV-1 RNA less than 400 copies/mL was 67%. The mean CD4+ cell count increase from baseline was 112 × 10^6cells/mm^3.

Pediatric Subjects (2 Years to Less Than 6 Years of Age [TMC125-C234/IMPAACT P1090])

TMC125-C234/IMPAACT P1090 is a Phase 1/2 trial evaluating the pharmacokinetics, safety, tolerability, and efficacy of Etravirine in 20 antiretroviral treatment-experienced HIV-1 infected pediatric subjects 2 years to less than 6 years of age. The study enrolled subjects who had virologic failure on an antiretroviral treatment regimen after at least 8 weeks of treatment, or who had interrupted treatment for at least 4 weeks. Enrolled subjects had a history of virologic failure while on an antiretroviral regimen, with a confirmed HIV-1 RNA plasma viral load greater than 1,000 copies/mL and with no evidence of phenotypic resistance to etravirine at screening.

The median baseline plasma HIV-1 RNA was 4.4 log10copies/mL, the median baseline CD4+ cell count was 817.5 × 10^6cells/mm^3, and the median baseline CD4+ percentage was 28%.

Virologic response, defined as achieving plasma viral load less than 400 HIV-1 RNA copies/mL, was evaluated.

Study treatment included etravirine plus an optimized background regimen of antiretroviral drugs. In addition to etravirine, all 20 subjects received a ritonavir-boosted protease inhibitor in combination with 1 or 2 NRTIs (n=14) and/or in combination with an integrase inhibitor (n=7).

At the time of the Week 24 analysis, seventeen subjects had completed at least 24 weeks of treatment or discontinued earlier. At Week 24, the proportion of subjects with less than 400 HIV-1 RNA copies/mL was 88% (15/17), and the proportion of subjects with less than 50 HIV-1 RNA copies/mL was 50% (7/14), for those with available data. The median change in plasma HIV-1 RNA from baseline to Week 24 was -2.14 log10copies/mL. The median CD4+ cell count increase and the median CD4+ percentage increase from baseline was 298 × 10^6cells/mm^3and 5%, respectively.

16 HOW SUPPLIED/STORAGE AND HANDLING

Etravirine 100 mg tablets are supplied as white to off-white, oval tablets containing 100 mg of etravirine. Each tablet is debossed with "TMC125" on one side and "100" on the other side.

Etravirine 200 mg tablets are supplied as white to off-white, biconvex, oblong tablets containing 200 mg of etravirine. Each tablet is debossed with "T200" on one side.

Etravirine tablets are packaged in bottles in the following configuration:

- 100 mg tablets—bottles of 120 (NDC 10147-0570-1). Each bottle contains 3 desiccant pouches.
- 200 mg tablets—bottles of 60 (NDC 10147-0571-1). Each bottle contains 3 desiccant pouches.

STORAGE AND HANDLING

Store Etravirine tablets at 25°C (77°F); with excursions permitted to 15° to 30°C (59° to 86°F) [see USP controlled room temperature]. Store in the original bottle. Keep the bottle tightly closed in order to protect from moisture. Do not remove the desiccant pouches.

Keep Etravirine and all medicines out of the reach of children.

17 PATIENT COUNSELING INFORMATION

Advise the patient to read the FDA-approved patient labeling (Patient Information).

Administration

Advise patients to take Etravirine following a meal twice a day on a regular dosing schedule, as missed doses can result in development of resistance. The type of food does not affect the exposure to etravirine. Inform patients not to take more or less than the prescribed dose of Etravirine or discontinue therapy with Etravirine without consulting their physician. Etravirine must always be used in combination with other antiretroviral drugs [see Dosage and Administration (2.4)].

Advise patients to swallow the Etravirine tablet(s) whole with a liquid such as water. Instruct patients not to chew the tablets. Patients who are unable to swallow the Etravirine tablet(s) whole may disperse the tablet(s) in water. The patient should be instructed to do the following:

- place the tablet(s) in 5 mL (1 teaspoon) of water, or at least enough liquid to cover the medication,
- stir well until the water looks milky,
- add approximately 15 mL (1 tablespoon) of liquid. Water may be used, but orange juice or milk may improve taste. Patients should not place the tablets in orange juice or milk without first adding water. The use of warm (temperature greater than 104°F [greater than 40°C]) or carbonated beverages should be avoided.
- drink the mixture immediately,
- rinse the glass several times with orange juice, milk or water and completely swallow the rinse each time to make sure the patient takes the entire dose.

Severe Skin Reactions

Inform patients that severe and potentially life-threatening rash has been reported with Etravirine. Rash has been reported most commonly in the first 6 weeks of therapy. Advise patients to immediately contact their healthcare provider if they develop rash. Instruct patients to immediately stop taking Etravirine and seek medical attention if they develop a rash associated with any of the following symptoms as it may be a sign of a more serious reaction such as Stevens-Johnson syndrome, toxic epidermal necrolysis or severe hypersensitivity: fever, generally ill feeling, extreme tiredness, muscle or joint aches, blisters, oral lesions, eye inflammation, facial swelling, swelling of the eyes, lips, mouth, breathing difficulty, and/or signs and symptoms of liver problems (e.g., yellowing of your skin or whites of your eyes, dark or tea colored urine, pale colored stools/bowel movements, nausea, vomiting, loss of appetite, or pain, aching or sensitivity on your right side below your ribs). Patients should understand that if severe rash occurs, they will be closely monitored, laboratory tests will be ordered and appropriate therapy will be initiated [see Warnings and Precautions (5.1)] .

Drug Interactions

Etravirine may interact with many drugs; therefore, advise patients to report to their healthcare provider the use of any other prescription or nonprescription medication or herbal products, including St. John's wort [see Warnings and Precautions (5.2)] .

Immune Reconstitution Syndrome

Advise patients to inform their healthcare provider immediately of any symptoms of infection, as in some patients with advanced HIV infection (AIDS), signs and symptoms of inflammation from previous infections may occur soon after anti-HIV treatment is started [see Warnings and Precautions (5.3)].

Fat Redistribution

Inform patients that redistribution or accumulation of body fat may occur in patients receiving antiretroviral therapy, including Etravirine, and that the cause and long-term health effects of these conditions are not known at this time [see Warnings and Precautions (5.4)] .

Pregnancy Registry

Inform patients that there is an antiretroviral pregnancy registry to monitor fetal outcomes of pregnant individuals exposed to Etravirine [see Use in Specific Populations (8.1)] .

Lactation

Instruct mothers with HIV-1 infection not to breastfeed because HIV-1 can be passed to the baby in breast milk [see Use in Specific Populations (8.2)] .

Manufactured for:
Patriot Pharmaceuticals, LLC
Horsham, PA 19044, USA

For patent information: www.janssenpatents.com

PATIENT INFORMATION
ETRAVIRINE
tablets

Important: Ask your healthcare provider or pharmacist about medicines that should not be taken with Etravirine. For more information, see the section "What should I tell my healthcare provider before taking Etravirine?"

What is Etravirine?

Etravirine is a prescription medicine that is used to treat human immunodeficiency virus-1 (HIV-1) infection in combination with other HIV-1 medicines, in adults and children 2 years of age and older who have taken HIV-1 medicines in the past.

HIV-1 is the virus that causes AIDS (Acquired Immune Deficiency Syndrome).

Etravirine is not recommended for use in children less than 2 years of age.

What should I tell my healthcare provider before taking Etravirine?

Before taking Etravirine tell your healthcare provider about all of your medical conditions, including if you:

- have liver problems, including hepatitis B or C.
- are pregnant or plan to become pregnant. Tell your healthcare provider if you become pregnant during treatment with Etravirine.
  Pregnancy Registry:There is a pregnancy registry for people who take Etravirine during pregnancy. The purpose of this registry is to collect information about the health of you and your baby. Talk to your healthcare provider about how you can take part in this registry.
- are breastfeeding or plan to breastfeed. Do not breastfeed if you take Etravirine.
  - You should not breastfeed if you have HIV-1 because of the risk of passing HIV-1 to your baby.
  - Etravirine can pass to your baby in your breast milk.
  - Talk with your healthcare provider about the best way to feed your baby.

Tell your healthcare provider about all the medicines you take,including prescription and over-the-counter medicines, vitamins, and herbal supplements.

Some medicines may interact with Etravirine. Keep a list of your medicines and show it to your healthcare provider and pharmacist when you get a new medicine.

- You can ask your healthcare provider or pharmacist for a list of medicines that interact with Etravirine.
- Do not start a new medicine without telling your healthcare provider.Your healthcare provider can tell you if it is safe to take Etravirine with other medicines.

How should I take Etravirine?

- Stay under the care of your healthcare provider during treatment with Etravirine.
- Take Etravirine tablets every day exactly as prescribed by your healthcare provider.
- Your healthcare provider will tell you how many Etravirine tablets to take and when to take them. Talk to your healthcare provider if you have questions about when to take Etravirine.
- Take Etravirine 2 times each day.
- If your child takes Etravirine, your healthcare provider will prescribe the right dose based on your child's weight.
- Always take Etravirine following a meal.Do not take Etravirine on an empty stomach. Etravirine may not work as well if you take it on an empty stomach.
- Do not change your dose or stop taking Etravirine without first talking with your healthcare provider.
- Swallow Etravirine tablets whole, with liquid, such as water. Do not chew the tablet(s).
- If you are unable to swallow Etravirine tablets whole, you may take your dose of Etravirine as follows:
  Step 1: Measure approximately 5 mL (1 teaspoon) of water and pour into a cup.
  Step 2: Place the tablets in the cup containing 5 mL of water. If needed, add more water to cover the tablets. Do not put the tablets in other liquids.
  Step 3: Stir well until the water looks milky.
  Step 4: Add a small amount (approximately 15 mL or 1 tablespoon) of liquid. Water may be used but adding orange juice or milk rather than water may make it easier to take. Do not use warm (temperature more than 104°F or 40°C) or carbonated beverages.
  Step 5: Drink the mixture right away.
  Step 6: Add more orange juice, milk, or water to the cup to rinse the cup several times and completely swallow each time to make sure you take your entire dose of Etravirine.
- It is important that you do not miss or skip doses of Etravirine during treatment.
- When your supply of Etravirine starts to run low, get more from your healthcare provider or pharmacy. It is important not to run out of Etravirine. The amount of HIV in your blood may increase if the medicine is stopped even for a short time.
- If you take too much Etravirine, call your healthcare provider or go to the nearest emergency room right away.

What are the possible side effects of Etravirine?

Etravirine can cause serious side effects including:

- Severe skin rash and allergic reactions.Skin rash is a common side effect of Etravirine. The risk of getting a skin rash is higher in females. Rarely, rash can be severe and may lead to death. Severe skin rash with blisters or peeling skin, including the area around the mouth or eyes, may happen more frequently in children less than 18 years of age who take Etravirine in combination with other HIV-1 medicines than in adults. Call your healthcare provider right away if a rash develops; severe cases may need to be treated in a hospital.

If you get a rash with any of the following symptoms, stop taking Etravirine and call your healthcare provider or get medical help right away:

- fever
- generally ill feeling
- extreme tiredness

- muscle or joint aches
- blisters or sores in mouth
- blisters or peeling of the skin

- redness or swelling of the eyes
- swelling of the mouth, lips, or face
- problems breathing

Sometimes allergic reactions can affect body organs, such as your liver. Call your healthcare provider right away if you have any of the following signs or symptoms of liver problems:

- yellowing of your skin or whites of your eyes
- dark or tea colored urine
- pale colored stools (bowel movements)

- nausea or vomiting
- loss of appetite
- pain, aching, or tenderness on the right side of your stomach area

- Changes in your immune system (Immune Reconstitution Syndrome)can happen when you start taking HIV-1 medicines. Your immune system may get stronger and begin to fight infections that have been hidden in your body for a long time. Call your healthcare provider right away if you start having any new symptoms after starting your HIV-1 medicines.
- Changes in body fatcan happen in people taking HIV-1 medicines. These changes may include an increased amount of fat in the upper back and neck ("buffalo hump"), breast, and around the middle of your body (trunk). Loss of fat from the legs, arms, and face may also happen. The exact cause and long-term health effects of these problems are not known.

The most common side effects of Etravirine in adults include rash as well as numbness, tingling or pain in the hands or feet.

The most common side effects of Etravirine in children include rash and diarrhea.

These are not all the possible side effects of Etravirine.

Call your doctor for medical advice about side effects. You may report side effects to FDA at 1-800-FDA-1088.

How should I store Etravirine?

- Store Etravirine tablets at room temperature between 68°F to 77°F (20°C to 25°C).
- Keep Etravirine in the original bottle.
- Keep the bottle tightly closed to protect Etravirine from moisture.
- The Etravirine bottle contains a desiccant packet to help keep your medicine dry (protect it from moisture). The bottles of 100 mg and 200 mg tablets contain 3 desiccant packets. Keep the desiccant packets in the bottle. Do not eat the desiccant packets.

Keep Etravirine and all medicines out of the reach of children.

General information about the safe and effective use of Etravirine

Medicines are sometimes prescribed for purposes other than those listed in a Patient Information leaflet. Do not use Etravirine for a condition for which it was not prescribed. Do not give Etravirine to other people, even if they have the same symptoms that you have. It may harm them. You can ask your healthcare provider or pharmacist for information about Etravirine that is written for health professionals.

What are the ingredients in Etravirine?

Active ingredient:etravirine.

100 mg Etravirine tablets contain the following inactive ingredients:colloidal silicon dioxide, croscarmellose sodium, hypromellose, lactose monohydrate, magnesium stearate, and microcrystalline cellulose.

200 mg Etravirine tablets contain the following inactive ingredients:colloidal silicon dioxide, croscarmellose sodium, hypromellose, magnesium stearate, microcrystalline cellulose, and silicified microcrystalline cellulose.

Manufactured for:
Patriot Pharmaceuticals, LLC, Horsham, PA 19044, USA
For patent information: www.janssenpatents.com

For more information, call Patriot Pharmaceuticals, LLC at 1-800-667-8570.

This Patient Information has been approved by the U.S. Food and Drug Administration.

Issued: April 2025

PRINCIPAL DISPLAY PANEL - 100 mg Tablet Bottle Label

120 Tablets

NDC 10147-0570-1

Etravirine
tablets

100 mg

Each tablet contains
100 mg of etravirine.

Rx only

PATRIOT
PHARMACEUTICALS LLC

ALERT: Find out about medicines that
should NOT be taken with Etravirine tablets
from your healthcare provider.

PRINCIPAL DISPLAY PANEL - 200 mg Tablet Bottle Label

60 Tablets

NDC 10147-0571-1

Etravirine
tablets

200 mg

Each tablet contains
200 mg of etravirine.

Rx only

PATRIOT
PHARMACEUTICALS LLC

ALERT: Find out about medicines that
should NOT be taken with Etravirine tablets
from your healthcare provider.